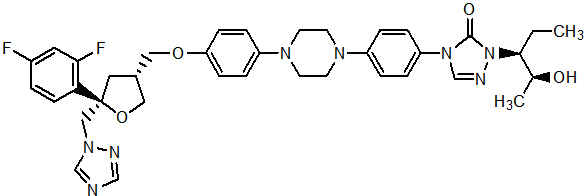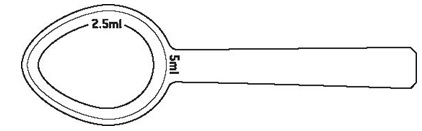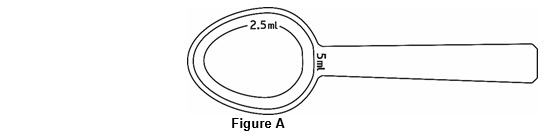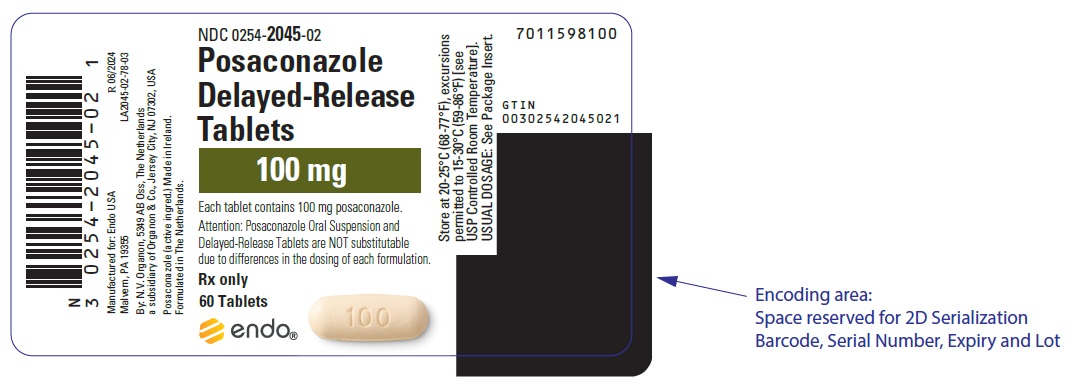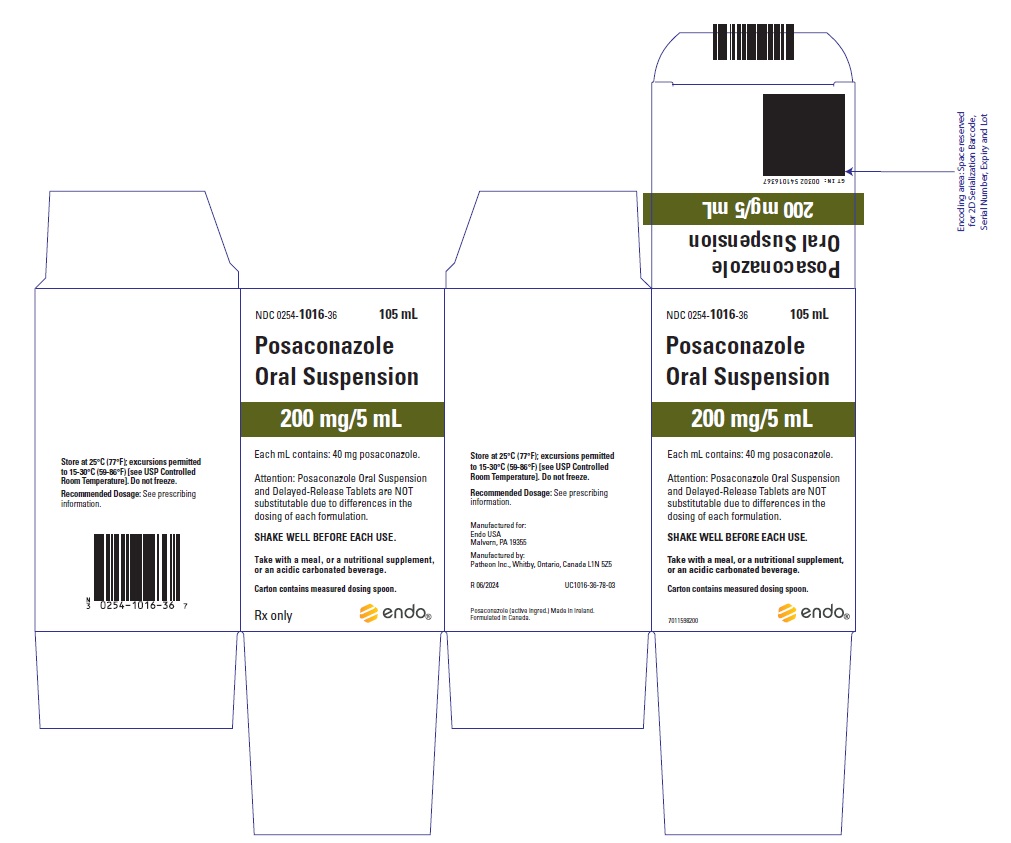 DRUG LABEL: POSACONAZOLE
NDC: 0254-2045 | Form: TABLET, COATED
Manufacturer: ENDO USA, Inc.
Category: prescription | Type: HUMAN PRESCRIPTION DRUG LABEL
Date: 20241113

ACTIVE INGREDIENTS: posaconazole 100 mg/1 1
INACTIVE INGREDIENTS: HYPROMELLOSE ACETATE SUCCINATE 06081224 (3 MM2/S); MICROCRYSTALLINE CELLULOSE; HYDROXYPROPYL CELLULOSE (1600000 WAMW); silicon dioxide; CROSCARMELLOSE SODIUM; MAGNESIUM STEARATE; POLYVINYL ALCOHOL, UNSPECIFIED; POLYETHYLENE GLYCOL 3350; TITANIUM DIOXIDE; TALC; FERRIC OXIDE YELLOW

HIGHLIGHTS OF PRESCRIBING INFORMATION

These highlights do not include all the information needed to use POSACONAZOLE safely and effectively. See full prescribing information for POSACONAZOLE.
Posaconazole delayed-release tablets, for oral use
Posaconazole oral suspension
Initial U.S. Approval: 2006

RECENT MAJOR CHANGES

Warnings and Precautions, Pseudoaldosteronism (5.4) | 10/2024

1 INDICATIONS AND USAGE

Posaconazole is an azole antifungal indicated as follows:

- Posaconazole delayed-release tablets are indicated for the treatment of invasive aspergillosis in adults and pediatric patients 13 years of age and older. (1.1)
- Posaconazole is indicated for the prophylaxis of invasive Aspergillus and Candida infections in patients who are at high risk of developing these infections due to being severely immunocompromised, such as hematopoietic stem cell transplant (HSCT) recipients with graft-versus-host disease (GVHD) or those with hematologic malignancies with prolonged neutropenia from chemotherapy as follows: (1.2)
  - Posaconazole delayed-release tablets: adults and pediatric patients 2 years of age and older who weigh greater than 40 kg
  - Posaconazole oral suspension: adults and pediatric patients 13 years of age and older
- Posaconazole oral suspension is indicated for the treatment of oropharyngeal candidiasis (OPC), including OPC refractory (rOPC) to itraconazole and/or fluconazole in adult and pediatric patients aged 13 years and older. (1.3)

2 DOSAGE AND ADMINISTRATION

- Posaconazole oral suspension is not substitutable with Posaconazole delayed-release tablets or Noxafil PowderMix for delayed-release oral suspension due to the differences in the dosing of each formulation. Therefore, follow the specific dosage recommendations for each of the formulations. (2.1, 2.2, 2.3)
- Administer Posaconazole delayed-release tablets with or without food. (2.1)
- Administer Posaconazole oral suspension with a full meal. (2.1)

Table 1: Recommended Dosage in Adult Patients
Indication | Dosage Form, Dose, and Duration of Therapy
Treatment of invasive Aspergillosis | Posaconazole Delayed-Release Tablets: Loading dose: 300 mg (three 100 mg delayed-release tablets) twice a day on the first day. Maintenance dose: 300 mg (three 100 mg delayed-release tablets) once a day thereafter. Recommended total duration of therapy is 6 to 12 weeks. (2.2) Switching between the intravenous and delayed-release tablets is acceptable. A loading dose is not required when switching between formulations. (2.2)
Prophylaxis of invasive Aspergillus and Candida infections | Posaconazole Delayed-Release Tablets: Loading dose: 300 mg (three 100 mg delayed-release tablets) twice a day on the first day. Maintenance dose: 300 mg (three 100 mg delayed-release tablets) once a day, starting on the second day. Duration of therapy is based on recovery from neutropenia or immunosuppression. (2.2, 2.3) Posaconazole Oral Suspension: 200 mg (5 mL) three times a day. Duration of therapy is based on recovery from neutropenia or immunosuppression. (2.2, 2.3)
Oropharyngeal Candidiasis (OPC) | Posaconazole Oral Suspension: Loading dose: 100 mg (2.5 mL) twice a day on the first day. Maintenance dose: 100 mg (2.5 mL) once a day for 13 days. (2.2, 2.3)
OPC Refractory (rOPC) to Itraconazole and/or Fluconazole | Posaconazole Oral Suspension: 400 mg (10 mL) twice a day. Duration of therapy is based on the severity of the patient’s underlying disease and clinical response. (2.2, 2.3)

- For pediatric patients, see the Full Prescribing Information for dosing recommendations for Posaconazole delayed-release tablets and Posaconazole oral suspension based on the age and indication associated with the dosage form. (1.1, 1.2, 1.3, 2.1, 2.3)

3 DOSAGE FORMS AND STRENGTHS

- Posaconazole delayed-release tablet: 100 mg (3)
- Posaconazole oral suspension: 40 mg per mL (3)

4 CONTRAINDICATIONS

- Known hypersensitivity to posaconazole or other azole antifungal agents. (4.1)
- Coadministration of posaconazole with the following drugs is contraindicated: posaconazole increases concentrations and toxicities of:
  - Sirolimus (4.2, 5.1, 7.1)
  - CYP3A4 substrates (pimozide, quinidine): can result in QTc interval prolongation and cases of torsades de pointes (TdP) (4.3, 5.2, 7.2)
  - HMG-CoA Reductase Inhibitors Primarily Metabolized through CYP3A4 (4.4, 7.3)
  - Ergot alkaloids (4.5, 7.4)
  - Venetoclax: In patients with chronic lymphocytic leukemia (CLL) or small lymphocytic lymphoma (SLL) at initiation and during the ramp-up phase (4.6, 5.10, 7.15)

5 WARNINGS AND PRECAUTIONS

- Calcineurin-Inhibitor Toxicity: Posaconazole increases concentrations of cyclosporine or tacrolimus; reduce dose of cyclosporine and tacrolimus and monitor concentrations frequently. (5.1)
- Arrhythmias and QTc Prolongation: Posaconazole has been shown to prolong the QTc interval and cause cases of TdP. Administer with caution to patients with potentially proarrhythmic conditions. Do not administer with drugs known to prolong QTc interval and metabolized through CYP3A4. (5.2)
- Electrolyte Disturbances: Monitor and correct, especially those involving potassium (K^+), magnesium (Mg^++), and calcium (Ca^++), before and during posaconazole therapy. (5.3)
- Pseudoaldosteronism: Manifested by the onset or worsening of hypertension, and abnormal laboratory findings. Monitor blood pressure and potassium levels, and manage as necessary. (5.4)
- Hepatic Toxicity: Elevations in liver tests may occur. Discontinuation should be considered in patients who develop abnormal liver tests or monitor liver tests during treatment. (5.5)
- Concomitant Use with Midazolam: Posaconazole can prolong hypnotic/sedative effects. Monitor patients and benzodiazepine receptor antagonists should be available. (5.7, 7.5)
- Vincristine Toxicity: Concomitant administration of azole antifungals, including posaconazole, with vincristine has been associated with neurotoxicity and other serious adverse reactions; reserve azole antifungals, including posaconazole, for patients receiving a vinca alkaloid, including vincristine, who have no alternative antifungal treatment options. (5.8, 7.10)
- Breakthrough Fungal Infections: Monitor patients with severe diarrhea or vomiting when receiving Posaconazole delayed-release tablets and Posaconazole oral suspension. (5.9)
- Venetoclax Toxicity: Concomitant administration of posaconazole with venetoclax may increase venetoclax toxicities, including the risk of tumor lysis syndrome, neutropenia, and serious infections; monitor for toxicity and reduce venetoclax dose. (4.6, 5.10, 7.15)

6 ADVERSE REACTIONS

- Common adverse reactions in studies with posaconazole are diarrhea, nausea, fever, vomiting, headache, coughing, and hypokalemia. (6.1)

To report SUSPECTED ADVERSE REACTIONS, contact Merck Sharp & Dohme LLC at 1-877-888-4231 or FDA at 1-800-FDA-1088 or www.fda.gov/medwatch .

7 DRUG INTERACTIONS

Interaction Drug | Interaction
Rifabutin, phenytoin, efavirenz, cimetidine, esomeprazole [The drug interactions with esomeprazole and metoclopramide do not apply to Posaconazole tablets.] | Avoid coadministration unless the benefit outweighs the risks (7.6, 7.7, 7.8, 7.9)
Other drugs metabolized by CYP3A4 | Consider dosage adjustment and monitor for adverse effects and toxicity (7.1, 7.10, 7.11)
Digoxin | Monitor digoxin plasma concentrations (7.12)
Fosamprenavir, metoclopramide | Monitor for breakthrough fungal infections (7.6, 7.13)

8 USE IN SPECIFIC POPULATIONS

- Pregnancy: Based on animal data, may cause fetal harm. (8.1)
- Pediatrics: Safety and effectiveness in patients younger than 2 years of age have not been established. (8.4)
- Severe Renal Impairment: Monitor closely for breakthrough fungal infections. (8.6)

FULL PRESCRIBING INFORMATION

1 INDICATIONS AND USAGE

1.1 Treatment of Invasive Aspergillosis

Posaconazole delayed-release tablets are indicated for the treatment of invasive aspergillosis in adults and pediatric patients 13 years of age and older.

1.2 Prophylaxis of Invasive Aspergillus and Candida Infections

Posaconazole is indicated for the prophylaxis of invasive Aspergillus and Candida infections in patients who are at high risk of developing these infections due to being severely immunocompromised, such as hematopoietic stem cell transplant (HSCT) recipients with graft-versus-host disease (GVHD) or those with hematologic malignancies with prolonged neutropenia from chemotherapy [see Clinical Studies (14.1)] as follows:

- Posaconazole delayed-release tablets: adults and pediatric patients 2 years of age and older who weigh greater than 40 kg
- Posaconazole oral suspension: adults and pediatric patients 13 years of age and older

1.3 Treatment of Oropharyngeal Candidiasis Including Oropharyngeal Candidiasis Refractory to Itraconazole and/or Fluconazole

Posaconazole oral suspension is indicated for the treatment of oropharyngeal candidiasis, including oropharyngeal candidiasis refractory to itraconazole and/or fluconazole in adults and pediatric patients 13 years of age and older.

2 DOSAGE AND ADMINISTRATION

2.1 Important Administration Instructions

Non-substitutable

Posaconazole oral suspension is not substitutable with Posaconazole delayed-release tablets or Noxafil PowderMix for delayed-release oral suspension due to the differences in the dosing of each formulation. Therefore, follow the specific dosage recommendations for each of the formulations [see Dosage and Administration (2.2, 2.3)].

Posaconazole delayed-release tablets

- Swallow tablets whole. Do not divide, crush, or chew.
- Administer with or without food [see Dosage and Administration (2.2) and Clinical Pharmacology (12.3)].
- For patients who cannot eat a full meal, Posaconazole delayed-release tablets should be used instead of Posaconazole oral suspension for the prophylaxis indication. Posaconazole delayed-release tablets generally provide higher plasma drug exposures than Posaconazole oral suspension under both fed and fasted conditions [see Dosage and Administration (2.5)].

Posaconazole oral suspension

- Administer with a full meal or with a liquid nutritional supplement or an acidic carbonated beverage (e.g., ginger ale) in patients who cannot eat a full meal [see Dosage and Administration (2.5)].
- Co-administration of drugs that can decrease the plasma concentrations of posaconazole should generally be avoided unless the benefit outweighs the risk. If such drugs are necessary, patients should be monitored closely for breakthrough fungal infections [see Drug Interactions (7.6, 7.7, 7.8, 7.9, 7.13)].

2.2 Dosing Regimen in Adult Patients

Table 1: Dosing Regimens in Adult Patients
Indication | Dose and Frequency | Duration of Therapy
Treatment of invasive Aspergillosis | Posaconazole Delayed-Release Tablets: Loading dose: 300 mg (three 100 mg delayed-release tablets) twice a day on the first day. Maintenance dose: 300 mg (three 100 mg delayed-release tablets) once a day, starting on the second day. Switching between the intravenous and delayed-release tablets is acceptable. A loading dose is not required when switching between formulations. | Loading dose: 1 day Maintenance dose: Recommended total duration of therapy is 6 to 12 weeks.
Prophylaxis of invasive Aspergillus and Candida infections | Posaconazole Delayed-Release Tablets: Loading dose: 300 mg (three 100 mg delayed-release tablets) twice a day on the first day. Maintenance dose: 300 mg (three 100 mg delayed-release tablets) once a day, starting on the second day. Posaconazole Oral Suspension: 200 mg (5 mL) three times a day. | Loading dose: 1 day Maintenance dose: Duration of therapy is based on recovery from neutropenia or immunosuppression.
Oropharyngeal Candidiasis (OPC) | Posaconazole Oral Suspension: Loading dose: 100 mg (2.5 mL) twice a day on the first day. Maintenance dose: 100 mg (2.5 mL) once a day thereafter. | Loading dose: 1 day Maintenance dose: 13 days
OPC Refractory (rOPC) to Itraconazole and/or Fluconazole | Posaconazole Oral Suspension: 400 mg (10 mL) twice a day. | Duration of therapy is based on the severity of the patient’s underlying disease and clinical response.

2.3 Dosing Regimen in Pediatric Patients (ages 2 to less than 18 years of age)

- The recommended dosing regimen of posaconazole for pediatric patients 2 to less than 18 years of age is shown in Tables 2 and 3 [see Dosage and Administration (2.4, 2.5) and Clinical Pharmacology (12.3)].

Table 2: Posaconazole Delayed-Release Tablet Dosing Regimens for Pediatric Patients (ages 2 to less than 18 years of age)
 |  | Recommended Pediatric Dosage and Formulation
Indication | Weight/Age | Delayed-Release Tablet | Duration of therapy
Prophylaxis of invasive Aspergillus and Candida infections | Less than or equal to 40 kg (2 to less than 18 years of age) | Not Applicable | Duration of therapy is based on recovery from neutropenia or immunosuppression.
Prophylaxis of invasive Aspergillus and Candida infections | Greater than 40 kg (2 to less than 18 years of age) | Loading dose: 300 mg twice daily on the first day Maintenance dose: 300 mg once daily | Duration of therapy is based on recovery from neutropenia or immunosuppression.
Treatment of invasive Aspergillosis | 13 to less than 18 years of age regardless of weight. | Loading dose: 300 mg (three 100 mg delayed-release tablets) twice a day on the first day. Maintenance dose: 300 mg (three 100 mg delayed-release tablets) once a day, starting on the second day. Switching between the intravenous and delayed-release tablets is acceptable. A loading dose is not required when switching between formulations. | Loading dose: 1 day Maintenance dose: Recommended total duration of therapy is 6 to 12 weeks.

Table 3: Posaconazole Oral Suspension Dosing Regimens for Pediatric Patients (ages 13 to less than 18 years of age)
Indication | Loading Dose (volume) and frequency | Maintenance Dose (volume) and frequency | Duration of therapy
Prophylaxis of invasive Aspergillus and Candida infections | 200 mg (5 mL) three times a day | 200 mg (5 mL) three times a day | Duration of therapy is based on recovery from neutropenia or immunosuppression.
Oropharyngeal Candidiasis (OPC) | 100 mg (2.5 mL) twice daily on the first day | 100 mg (2.5 mL) once daily | 13 days
OPC Refractory (rOPC) to Itraconazole and/or Fluconazole | 400 mg (10 mL) twice daily | 400 mg (10 mL) twice daily | Duration of therapy is based on the severity of the patient’s underlying disease and clinical response.

2.4 Administration Instructions for Posaconazole Delayed-Release Tablets

- Swallow tablets whole. Do not divide, crush, or chew.
- Administer Posaconazole delayed-release tablets with or without food [see Clinical Pharmacology (12.3)].

2.5 Administration Instructions for Posaconazole Oral Suspension

- Shake Posaconazole oral suspension well before use. Administer with measured dosing spoon (see Figure 1) provided.

Figure 1: A measured dosing spoon is provided, marked for doses of 2.5 mL and 5 mL.

- Rinse the spoon with water after each administration and before storage.
- Administer each dose of Posaconazole oral suspension during or immediately (i.e., within 20 minutes) following a full meal [see Clinical Pharmacology (12.3)].
- For patients who cannot eat a full meal, Posaconazole delayed-release tablets should be used instead of Posaconazole oral suspension for the prophylaxis indication. Posaconazole delayed-release tablets provide higher plasma drug exposures than Posaconazole oral suspension under fasted conditions [see Dosage and Administration (2.1)].
- In patients who cannot eat a full meal and for whom Posaconazole delayed-release tablets or Noxafil injection are not options, administer each dose of Posaconazole oral suspension with a liquid nutritional supplement or an acidic carbonated beverage (e.g., ginger ale).
- For patients who cannot eat a full meal or tolerate an oral nutritional supplement or an acidic carbonated beverage and who do not have the option of taking Posaconazole delayed-release tablets or Noxafil injection, an alternative antifungal therapy should be considered or patients should be monitored closely for breakthrough fungal infections.

2.6 Non-substitutability between Posaconazole Oral Suspension and Other Formulations

Posaconazole oral suspension is not substitutable with Posaconazole delayed-release tablets or Noxafil PowderMix for delayed-release oral suspension due to the differences in the dosing of each formulation. Therefore, follow the specific dosage recommendations for each of the formulations [see Dosage and Administration (2.2, 2.3)].

2.7 Dosage Adjustments in Patients with Renal Impairment

The pharmacokinetics of Posaconazole oral suspension and Posaconazole delayed-release tablets are not significantly affected by renal impairment. Therefore, no adjustment is necessary for oral dosing in patients with mild to severe renal impairment.

3 DOSAGE FORMS AND STRENGTHS

Posaconazole Delayed-Release Tablets

Posaconazole delayed-release tablets are available as yellow, coated, oblong tablets, debossed with "100" on one side containing 100 mg of posaconazole.

Posaconazole Oral Suspension

Posaconazole oral suspension is available as a white, cherry-flavored suspension in 4-ounce (123 mL) amber glass bottles with child-resistant closures containing 105 mL of suspension (40 mg of posaconazole per mL).

4 CONTRAINDICATIONS

4.1 Hypersensitivity

Posaconazole is contraindicated in persons with known hypersensitivity to posaconazole or other azole antifungal agents.

4.2 Use with Sirolimus

Posaconazole is contraindicated with sirolimus. Concomitant administration of posaconazole with sirolimus increases the sirolimus blood concentrations by approximately 9-fold and can result in sirolimus toxicity [see Drug Interactions (7.1) and Clinical Pharmacology (12.3)].

4.3 QT Prolongation with Concomitant Use with CYP3A4 Substrates

Posaconazole is contraindicated with CYP3A4 substrates that prolong the QT interval. Concomitant administration of posaconazole with the CYP3A4 substrates, pimozide and quinidine may result in increased plasma concentrations of these drugs, leading to QTc prolongation and cases of torsades de pointes [see Warnings and Precautions (5.2) and Drug Interactions (7.2)].

4.4 HMG-CoA Reductase Inhibitors Primarily Metabolized Through CYP3A4

Coadministration with the HMG-CoA reductase inhibitors that are primarily metabolized through CYP3A4 (e.g., atorvastatin, lovastatin, and simvastatin) is contraindicated since increased plasma concentration of these drugs can lead to rhabdomyolysis [see Drug Interactions (7.3) and Clinical Pharmacology (12.3)].

4.5 Use with Ergot Alkaloids

Posaconazole may increase the plasma concentrations of ergot alkaloids (ergotamine and dihydroergotamine) which may lead to ergotism [see Drug Interactions (7.4)].

4.6 Use with Venetoclax

Coadministration of posaconazole with venetoclax at initiation and during the ramp-up phase is contraindicated in patients with chronic lymphocytic leukemia (CLL) or small lymphocytic lymphoma (SLL) due to the potential for increased risk of tumor lysis syndrome [see Warnings and Precautions (5.10) and Drug Interactions (7.15)].

5 WARNINGS AND PRECAUTIONS

5.1 Calcineurin-Inhibitor Toxicity

Concomitant administration of posaconazole with cyclosporine or tacrolimus increases the whole blood trough concentrations of these calcineurin-inhibitors [see Drug Interactions (7.1) and Clinical Pharmacology (12.3)]. Nephrotoxicity and leukoencephalopathy (including deaths) have been reported in clinical efficacy studies in patients with elevated cyclosporine or tacrolimus concentrations. Frequent monitoring of tacrolimus or cyclosporine whole blood trough concentrations should be performed during and at discontinuation of posaconazole treatment and the tacrolimus or cyclosporine dose adjusted accordingly.

5.2 Arrhythmias and QT Prolongation

Some azoles, including posaconazole, have been associated with prolongation of the QT interval on the electrocardiogram. In addition, cases of torsades de pointes have been reported in patients taking posaconazole.

Results from a multiple time-matched ECG analysis in healthy volunteers did not show any increase in the mean of the QTc interval. Multiple, time-matched ECGs collected over a 12-hour period were recorded at baseline and steady-state from 173 healthy male and female volunteers (18-85 years of age) administered Noxafil oral suspension 400 mg twice daily with a high-fat meal. In this pooled analysis, the mean QTc (Fridericia) interval change from baseline was –5 msec following administration of the recommended clinical dose. A decrease in the QTc(F) interval (–3 msec) was also observed in a small number of subjects (n=16) administered placebo. The placebo-adjusted mean maximum QTc(F) interval change from baseline was <0 msec (–8 msec). No healthy subject administered Noxafil had a QTc(F) interval ≥500 msec or an increase ≥60 msec in their QTc(F) interval from baseline.

Posaconazole should be administered with caution to patients with potentially proarrhythmic conditions. Do not administer with drugs that are known to prolong the QTc interval and are metabolized through CYP3A4 [see Contraindications (4.3) and Drug Interactions (7.2)].

5.3 Electrolyte Disturbances

Electrolyte disturbances, especially those involving potassium, magnesium or calcium levels, should be monitored and corrected as necessary before and during posaconazole therapy.

5.4 Pseudoaldosteronism

Pseudoaldosteronism, manifested by the onset of hypertension or worsening of hypertension, and abnormal laboratory findings (hypokalemia, low serum renin and aldosterone, and elevated 11-deoxycortisol), has been reported with posaconazole use in the postmarket setting. Monitor blood pressure and potassium levels and manage as necessary. Management of pseudoaldosteronism may include discontinuation of posaconazole, substitution with an appropriate antifungal drug that is not associated with pseudoaldosteronism, or use of aldosterone receptor antagonists.

5.5 Hepatic Toxicity

Hepatic reactions (e.g., mild to moderate elevations in alanine aminotransferase (ALT), aspartate aminotransferase (AST), alkaline phosphatase, total bilirubin, and/or clinical hepatitis) have been reported in clinical trials. The elevations in liver tests were generally reversible on discontinuation of therapy, and in some instances these tests normalized without drug interruption. Cases of more severe hepatic reactions including cholestasis or hepatic failure including deaths have been reported in patients with serious underlying medical conditions (e.g., hematologic malignancy) during treatment with posaconazole. These severe hepatic reactions were seen primarily in subjects receiving the Posaconazole oral suspension 800 mg daily (400 mg twice daily or 200 mg four times a day) in clinical trials.

Liver tests should be evaluated at the start of and during the course of posaconazole therapy. Patients who develop abnormal liver tests during posaconazole therapy should be monitored for the development of more severe hepatic injury. Patient management should include laboratory evaluation of hepatic function (particularly liver tests and bilirubin). Discontinuation of posaconazole must be considered if clinical signs and symptoms consistent with liver disease develop that may be attributable to posaconazole.

5.6 Renal Impairment

Due to the variability in exposure with Posaconazole delayed-release tablets and Posaconazole oral suspension, patients with severe renal impairment should be monitored closely for breakthrough fungal infections [see Dosage and Administration (2.4) and Use in Specific Populations (8.6)].

5.7 Midazolam Toxicity

Concomitant administration of posaconazole with midazolam increases the midazolam plasma concentrations by approximately 5-fold. Increased plasma midazolam concentrations could potentiate and prolong hypnotic and sedative effects. Patients must be monitored closely for adverse effects associated with high plasma concentrations of midazolam and benzodiazepine receptor antagonists must be available to reverse these effects [see Drug Interactions (7.5) and Clinical Pharmacology (12.3)].

5.8 Vincristine Toxicity

Concomitant administration of azole antifungals, including posaconazole, with vincristine has been associated with neurotoxicity and other serious adverse reactions, including seizures, peripheral neuropathy, syndrome of inappropriate antidiuretic hormone secretion, and paralytic ileus. Reserve azole antifungals, including posaconazole, for patients receiving a vinca alkaloid, including vincristine, who have no alternative antifungal treatment options [see Drug Interactions (7.10)].

5.9 Breakthrough Fungal Infections

Patients who have severe diarrhea or vomiting should be monitored closely for breakthrough fungal infections when receiving Posaconazole delayed-release tablets or Posaconazole oral suspension.

5.10 Venetoclax Toxicity

Concomitant administration of posaconazole, a strong CYP3A4 inhibitor, with venetoclax may increase venetoclax toxicities, including the risk of tumor lysis syndrome (TLS), neutropenia, and serious infections. In patients with CLL/SLL, administration of posaconazole during initiation and the ramp-up phase of venetoclax is contraindicated [see Contraindications (4.6)]. Refer to the venetoclax labeling for safety monitoring and dose reduction in the steady daily dosing phase in CLL/SLL patients.

For patients with acute myeloid leukemia (AML), dose reduction and safety monitoring are recommended across all dosing phases when coadministering posaconazole with venetoclax [see Drug Interactions (7.15)]. Refer to the venetoclax prescribing information for dosing instructions.

6 ADVERSE REACTIONS

The following serious and otherwise important adverse reactions are discussed in detail in another section of the labeling:

- Hypersensitivity [see Contraindications (4.1)]
- Arrhythmias and QT Prolongation [see Warnings and Precautions (5.2)]
- Hepatic Toxicity [see Warnings and Precautions (5.5)]

6.1 Clinical Trials Experience

Because clinical trials are conducted under widely varying conditions, adverse reaction rates observed in clinical trials of Noxafil cannot be directly compared to rates in the clinical trials of another drug and may not reflect the rates observed in practice.

Clinical Trial Experience in Adults

Clinical Trial Experience with Noxafil Injection and Noxafil Delayed-Release Tablets for the Treatment of Invasive Aspergillosis

The safety of Noxafil injection and Noxafil delayed-release tablet was assessed in a randomized, double-blind, active-controlled clinical study of Noxafil injection and Noxafil delayed-release tablets versus voriconazole for treatment of invasive aspergillosis (Aspergillosis Treatment Study). A total of 575 (288 in Noxafil arm, 287 in voriconazole arm) adult and pediatric patients 13 years of age and older with proven, probable or possible invasive aspergillosis were included. The median duration of treatment was 67 days for Noxafil injection or Noxafil delayed-release tablet and 64 days for voriconazole, with 55% to 60% of subjects starting treatment with the IV formulation of either drug. The median duration of the first instance of IV treatment (before switching to oral treatment or discontinuing or completing study treatment) was 9 days for both groups. Table 4 presents adverse reactions reported at an incidence of ≥10% in either one of the groups in Aspergillosis Treatment Study.

Adverse reactions leading to treatment discontinuation were reported for 33.9% of subjects. The most commonly reported adverse reactions (>2% of subjects) leading to treatment discontinuation were septic shock, respiratory failure, and bronchopulmonary aspergillosis in the Noxafil arm, and septic shock and acute myeloid leukemia in the voriconazole arm.

Table 4: Noxafil Invasive Aspergillosis Treatment Study: Adverse Reactions in at Least 10% of Subjects Treated with Noxafil Injection or Noxafil Delayed-Release Tablets
System Organ Class | Noxafil injection or tablet (N = 288), n (%) | Voriconazole injection or oral (N = 287), n (%)
Blood and lymphatic system disorders
Anemia | 25 (8.7) | 29 (10.1)
Febrile neutropenia | 42 (14.6) | 38 (13.2)
Gastrointestinal disorders
Abdominal pain | 29 (10.1) | 24 (8.4)
Constipation | 32 (11.1) | 23 (8.0)
Diarrhea | 52 (18.1) | 52 (18.1)
Nausea | 65 (22.6) | 51 (17.8)
Vomiting | 52 (18.1) | 39 (13.6)
General disorders and administration site conditions
Edema peripheral | 32 (11.1) | 24 (8.4)
Pyrexia | 81 (28.1) | 72 (25.1)
Infections and infestations
Pneumonia | 36 (12.5) | 26 (9.1)
Investigations
Alanine aminotransferase increased | 42 (14.6) | 37 (12.9)
Aspartate aminotransferase increased | 38 (13.2) | 36 (12.5)
Blood alkaline phosphatase increased | 21 (7.3) | 29 (10.1)
Metabolism and nutrition disorders
Hypokalemia | 82 (28.5) | 49 (17.1)
Hypomagnesemia | 29 (10.1) | 18 (6.3)
Nervous system disorders
Headache | 35 (12.2) | 25 (8.7)
Respiratory, thoracic and mediastinal disorders
Cough | 30 (10.4) | 24 (8.4)
Epistaxis | 32 (11.1) | 17 (5.9)

The most frequently reported adverse reactions in the Noxafil-treated group were pyrexia (28%), hypokalemia (28%), and nausea (23%).

Clinical Trial Experience with Noxafil Delayed-Release Tablets for Prophylaxis

The safety of Noxafil delayed-release tablets has been assessed in 230 patients in clinical trials. Patients were enrolled in a non-comparative pharmacokinetic and safety trial of Noxafil delayed-release tablets when given as antifungal prophylaxis (Noxafil Delayed-Release Tablet Study). Patients were immunocompromised with underlying conditions including hematological malignancy, neutropenia post-chemotherapy, GVHD, and post HSCT. This patient population was 62% male, had a mean age of 51 years (range 19-78 years, 17% of patients were ≥65 years of age), and were 93% white and 16% Hispanic. Posaconazole therapy was given for a median duration of 28 days. Twenty patients received 200 mg daily dose and 210 patients received 300 mg daily dose (following twice daily dosing on Day 1 in each cohort). Table 5 presents adverse reactions observed in patients treated with 300 mg daily dose at an incidence of ≥10% in Noxafil Delayed-Release Tablet Study.

Table 5: Noxafil Delayed-Release Tablet Study: Adverse Reactions in at Least 10% of Subjects Treated with 300 mg Daily Dose
Body System | Noxafil delayed-release tablet (300 mg) n=210 (%)
Subjects Reporting any Adverse Reaction | 207 | (99)
Blood and Lymphatic System Disorder
Anemia | 22 | (10)
Thrombocytopenia | 29 | (14)
Gastrointestinal Disorders
Abdominal Pain | 23 | (11)
Constipation | 20 | (10)
Diarrhea | 61 | (29)
Nausea | 56 | (27)
Vomiting | 28 | (13)
General Disorders and Administration Site Conditions
Asthenia | 20 | (10)
Chills | 22 | (10)
Mucosal Inflammation | 29 | (14)
Edema Peripheral | 33 | (16)
Pyrexia | 59 | (28)
Metabolism and Nutrition Disorders
Hypokalemia | 46 | (22)
Hypomagnesemia | 20 | (10)
Nervous System Disorders
Headache | 30 | (14)
Respiratory, Thoracic and Mediastinal Disorders
Cough | 35 | (17)
Epistaxis | 30 | (14)
Skin and Subcutaneous Tissue Disorders
Rash | 34 | (16)
Vascular Disorders
Hypertension | 23 | (11)

The most frequently reported adverse reactions (>25%) with Noxafil delayed-release tablets 300 mg once daily were diarrhea, pyrexia, and nausea.

The most common adverse reaction leading to discontinuation of Noxafil delayed-release tablets 300 mg once daily was nausea (2%).

Clinical Trial Safety Experience with Noxafil Oral Suspension

The safety of Noxafil oral suspension has been assessed in 1844 patients. This includes 605 patients in the active-controlled prophylaxis studies, 557 patients in the active-controlled OPC studies, 239 patients in refractory OPC studies, and 443 patients from other indications. This represents a heterogeneous population, including immunocompromised patients, e.g., patients with hematological malignancy, neutropenia post-chemotherapy, GVHD post HSCT, and HIV infection, as well as non-neutropenic patients. This patient population was 71% male, had a mean age of 42 years (range 8-84 years, 6% of patients were ≥65 years of age and 1% was <18 years of age), and were 64% white, 16% Hispanic, and 36% non-white (including 14% black). Noxafil therapy was given to 171 patients for ≥6 months, with 58 patients receiving Noxafil therapy for ≥12 months. Table 6 presents adverse reactions observed at an incidence of >10% in Noxafil prophylaxis studies. Table 7 presents adverse reactions observed at an incidence of at least 10% in the OPC/rOPC studies.

Prophylaxis of Aspergillus and Candida: In the 2 randomized, comparative prophylaxis studies (Noxafil Oral Suspension Study 1 and 2), the safety of Noxafil oral suspension 200 mg three times a day was compared to fluconazole 400 mg once daily or itraconazole 200 mg twice a day in severely immunocompromised patients.

The most frequently reported adverse reactions (>30%) in the prophylaxis clinical trials were fever, diarrhea, and nausea.

The most common adverse reactions leading to discontinuation of Noxafil in the prophylaxis studies were associated with GI disorders, specifically, nausea (2%), vomiting (2%), and hepatic enzymes increased (2%).

Table 6: Noxafil Oral Suspension Study 1 and Study 2. Adverse Reactions in at Least 10% of the Noxafil Oral Suspension or Fluconazole Treatment Groups (Pooled Prophylaxis Safety Analysis)
Body System | Noxafil Oral Suspension n=605 (%) |  | Fluconazole n=539 (%) |  | Itraconazole n=58 (%)
Subjects Reporting any Adverse Reaction | 595 | (98) | 531 | (99) | 58 | (100)
Body as a Whole - General Disorders
Fever | 274 | (45) | 254 | (47) | 32 | (55)
Headache | 171 | (28) | 141 | (26) | 23 | (40)
Rigors | 122 | (20) | 87 | (16) | 17 | (29)
Fatigue | 101 | (17) | 98 | (18) | 5 | (9)
Edema Legs | 93 | (15) | 67 | (12) | 11 | (19)
Anorexia | 92 | (15) | 94 | (17) | 16 | (28)
Dizziness | 64 | (11) | 56 | (10) | 5 | (9)
Edema | 54 | (9) | 68 | (13) | 8 | (14)
Weakness | 51 | (8) | 52 | (10) | 2 | (3)
Cardiovascular Disorders, General
Hypertension | 106 | (18) | 88 | (16) | 3 | (5)
Hypotension | 83 | (14) | 79 | (15) | 10 | (17)
Disorders of Blood and Lymphatic System
Anemia | 149 | (25) | 124 | (23) | 16 | (28)
Neutropenia | 141 | (23) | 122 | (23) | 23 | (40)
Disorders of the Reproductive System and Breast
Vaginal Hemorrhage [Percentages of sex-specific adverse reactions are based on the number of males/females.] | 24 | (10) | 20 | (9) | 3 | (12)
Gastrointestinal System Disorders
Diarrhea | 256 | (42) | 212 | (39) | 35 | (60)
Nausea | 232 | (38) | 198 | (37) | 30 | (52)
Vomiting | 174 | (29) | 173 | (32) | 24 | (41)
Abdominal Pain | 161 | (27) | 147 | (27) | 21 | (36)
Constipation | 126 | (21) | 94 | (17) | 10 | (17)
Dyspepsia | 61 | (10) | 50 | (9) | 6 | (10)
Heart Rate and Rhythm Disorders
Tachycardia | 72 | (12) | 75 | (14) | 3 | (5)
Infection and Infestations
Pharyngitis | 71 | (12) | 60 | (11) | 12 | (21)
Liver and Biliary System Disorders
Bilirubinemia | 59 | (10) | 51 | (9) | 11 | (19)
Metabolic and Nutritional Disorders
Hypokalemia | 181 | (30) | 142 | (26) | 30 | (52)
Hypomagnesemia | 110 | (18) | 84 | (16) | 11 | (19)
Hyperglycemia | 68 | (11) | 76 | (14) | 2 | (3)
Hypocalcemia | 56 | (9) | 55 | (10) | 5 | (9)
Musculoskeletal System Disorders
Musculoskeletal Pain | 95 | (16) | 82 | (15) | 9 | (16)
Arthralgia | 69 | (11) | 67 | (12) | 5 | (9)
Back Pain | 63 | (10) | 66 | (12) | 4 | (7)
Platelet, Bleeding and Clotting Disorders
Thrombocytopenia | 175 | (29) | 146 | (27) | 20 | (34)
Petechiae | 64 | (11) | 54 | (10) | 9 | (16)
Psychiatric Disorders
Insomnia | 103 | (17) | 92 | (17) | 11 | (19)
Respiratory System Disorders
Coughing | 146 | (24) | 130 | (24) | 14 | (24)
Dyspnea | 121 | (20) | 116 | (22) | 15 | (26)
Epistaxis | 82 | (14) | 73 | (14) | 12 | (21)
Skin and Subcutaneous Tissue Disorders
Rash | 113 | (19) | 96 | (18) | 25 | (43)
Pruritus | 69 | (11) | 62 | (12) | 11 | (19)

HIV Infected Subjects with OPC: In 2 randomized comparative studies in OPC, the safety of Noxafil oral suspension at a dose of less than or equal to 400 mg once daily in 557 HIV-infected patients was compared to the safety of fluconazole in 262 HIV-infected patients at a dose of 100 mg once daily.

An additional 239 HIV-infected patients with refractory OPC received Noxafil oral suspension in 2 non-comparative trials for refractory OPC (rOPC). Of these subjects, 149 received the 800-mg/day dose and the remainder received the less than or equal to 400 mg once daily dose.

In the OPC/rOPC studies, the most common adverse reactions were fever, diarrhea, nausea, headache, vomiting, and coughing.

The most common adverse reactions that led to treatment discontinuation of Noxafil in the Controlled OPC Pool included respiratory impairment (1%) and pneumonia (1%). In the refractory OPC pool, the most common adverse reactions that led to treatment discontinuation of Noxafil were AIDS (7%) and respiratory impairment (3%).

Table 7: Adverse Reactions in at Least 10% of the Treated Population in OPC Studies with Noxafil Oral Suspension
Body System | Number (%) of Subjects
Body System | Controlled OPC Pool |  | Refractory OPC Pool
Body System | Noxafil Oral Suspension | Fluconazole | Noxafil Oral Suspension
Body System | n=557 | n=262 | n=239
Subjects Reporting any Adverse Reaction [Number of subjects reporting adverse reactions at least once during the study, without regard to relationship to treatment. Subjects may have reported more than 1 event.] | 356 (64) | 175 (67) | 221 (92)
Body as a Whole – General Disorders
Fever | 34 (6) | 22 (8) | 82 (34)
Headache | 44 (8) | 23 (9) | 47 (20)
Anorexia | 10 (2) | 4 (2) | 46 (19)
Fatigue | 18 (3) | 12 (5) | 31 (13)
Asthenia | 9 (2) | 5 (2) | 31 (13)
Rigors | 2 (<1) | 4 (2) | 29 (12)
Pain | 4 (1) | 2 (1) | 27 (11)
Disorders of Blood and Lymphatic System
Neutropenia | 21 (4) | 8 (3) | 39 (16)
Anemia | 11 (2) | 5 (2) | 34 (14)
Gastrointestinal System Disorders
Diarrhea | 58 (10) | 34 (13) | 70 (29)
Nausea | 48 (9) | 30 (11) | 70 (29)
Vomiting | 37 (7) | 18 (7) | 67 (28)
Abdominal Pain | 27 (5) | 17 (6) | 43 (18)
Infection and Infestations
Candidiasis, Oral | 3 (1) | 1 (<1) | 28 (12)
Herpes Simplex | 16 (3) | 8 (3) | 26 (11)
Pneumonia | 17 (3) | 6 (2) | 25 (10)
Metabolic and Nutritional Disorders
Weight Decrease | 4 (1) | 2 (1) | 33 (14)
Dehydration | 4 (1) | 7 (3) | 27 (11)
Psychiatric Disorders
Insomnia | 8 (1) | 3 (1) | 39 (16)
Respiratory System Disorders
Coughing | 18 (3) | 11 (4) | 60 (25)
Dyspnea | 8 (1) | 8 (3) | 28 (12)
Skin and Subcutaneous Tissue Disorders
Rash | 15 (3) | 10 (4) | 36 (15)
Sweating Increased | 13 (2) | 5 (2) | 23 (10)
OPC=oropharyngeal candidiasis

Adverse reactions were reported more frequently in the pool of patients with refractory OPC. Among these highly immunocompromised patients with advanced HIV disease, serious adverse reactions (SARs) were reported in 55% (132/239). The most commonly reported SARs were fever (13%) and neutropenia (10%).

Other clinically significant adverse reactions reported in less than 5% of patients in clinical trials of Noxafil are listed below:

- Blood and lymphatic system disorders: hemolytic uremic syndrome, thrombotic thrombocytopenic purpura, neutropenia aggravated
- Endocrine disorders: adrenal insufficiency
- Nervous system disorders: paresthesia
- Immune system disorders: allergic reaction [see Contraindications (4.1)]
- Cardiac disorders: torsades de pointes [see Warnings and Precautions (5.2)]
- Vascular disorders: pulmonary embolism
- Gastrointestinal disorders: pancreatitis
- Liver and Biliary System Disorders: hepatic enzymes increased, hepatic function abnormal, hepatitis, hepatomegaly, jaundice
- Renal & Urinary System Disorders: renal failure acute

Clinical Laboratory Values: In healthy volunteers and patients, elevation of liver test values did not appear to be associated with higher plasma concentrations of posaconazole.

For the prophylaxis studies, the number of patients with changes in liver tests from Common Toxicity Criteria (CTC) Grade 0, 1, or 2 at baseline to Grade 3 or 4 during the study is presented in Table 8.

Table 8: Noxafil Oral Suspension Study 1 and Study 2. Changes in Liver Test Results from CTC Grade 0, 1, or 2 at Baseline to Grade 3 or 4
Number (%) of Patients with Change [Change from Grade 0 to 2 at baseline to Grade 3 or 4 during the study. These data are presented in the form X/Y, where X represents the number of patients who met the criterion as indicated, and Y represents the number of patients who had a baseline observation and at least one post-baseline observation.]
Noxafil Oral Suspension Study 1
Laboratory Parameter | Noxafil Oral Suspension n=301 | Fluconazole n=299
AST | 11/266 (4) | 13/266 (5)
ALT | 47/271 (17) | 39/272 (14)
Bilirubin | 24/271 (9) | 20/275 (7)
Alkaline Phosphatase | 9/271 (3) | 8/271 (3)
Noxafil Oral Suspension Study 2
Laboratory Parameter | Noxafil Oral Suspension (n=304) | Fluconazole/Itraconazole (n=298)
AST | 9/286 (3) | 5/280 (2)
ALT | 18/289 (6) | 13/284 (5)
Bilirubin | 20/290 (7) | 25/285 (9)
Alkaline Phosphatase | 4/281 (1) | 1/276 (<1)
CTC = Common Toxicity Criteria; AST= Aspartate Aminotransferase; ALT= Alanine Aminotransferase.

The number of patients treated for OPC with clinically significant liver test abnormalities at any time during the studies is provided in Table 9 (liver test abnormalities were present in some of these patients prior to initiation of the study drug).

Table 9: Noxafil Oral Suspension Studies: Clinically Significant Laboratory Test Abnormalities without Regard to Baseline Value
Laboratory Test | Controlled |  | Refractory
Laboratory Test | Noxafil Oral Suspension | Fluconazole | Noxafil Oral Suspension
Laboratory Test | n=557 (%) | n=262 (%) | n=239 (%)
ALT > 3.0 × ULN | 16/537 (3) | 13/254 (5) | 25/226 (11)
AST > 3.0 × ULN | 33/537 (6) | 26/254 (10) | 39/223 (17)
Total Bilirubin > 1.5 × ULN | 15/536 (3) | 5/254 (2) | 9/197 (5)
Alkaline Phosphatase > 3.0 × ULN | 17/535 (3) | 15/253 (6) | 24/190 (13)
ALT= Alanine Aminotransferase; AST= Aspartate Aminotransferase.

The number of patients treated for invasive aspergillosis with clinically significant liver test abnormalities at any time during the Aspergillosis Treatment Study is provided in Table 10. Liver test abnormalities present prior to the initiation of study drug included ALT (22%), AST (13%), and bilirubin (13%).

Table 10: Aspergillosis Treatment Study: Changes in Liver Test Results from CTC Grade 0, 1, or 2 at Baseline to Grade 3 or 4
Number (%) of Patients with Change [Change from Grade 0 to 2 at baseline to Grade 3 or 4 during the study. These data are presented in the form n/N, where n represents the number of patients who met the criterion as indicated, and N represents the number of patients who had a baseline observation and at least one post-baseline observation.]
Laboratory Parameter | Noxafil n/N (%) | Voriconazole n/N (%)
AST | 22/281 (8) | 21/285 (7)
ALT | 29/281(10) | 23/282 (8)
Bilirubin | 26/280 (9) | 25/284 (9)
Alkaline Phosphatase | 12/282 (4) | 20/284 (7)
N=Number of subjects for a given laboratory test with a baseline value of CTC Grade 0, 1, or 2 and at least one post-baseline value.
CTC = Common Toxicity Criteria; AST= Aspartate Aminotransferase; ALT= Alanine Aminotransferase.

Clinical Trial Experience in Pediatrics

Clinical Trial Experience in Pediatric Patients (2 to less than 18 Years of Age)

The safety of Noxafil injection and Noxafil PowderMix for delayed-release oral suspension for prophylaxis of invasive fungal infections has been assessed in an open label uncontrolled dose-ranging PK and safety study (Noxafil injection/ Noxafil PowderMix for delayed-release oral suspension Pediatric Study 1, NCT02452034); hereinafter referred to as Noxafil Pediatric Study) in 115 immunocompromised pediatric patients 2 to less than 18 years of age with known or expected neutropenia. Noxafil injection and Noxafil PowderMix for delayed-release oral suspension was administered at daily doses of up to 6 mg/kg (twice daily on day 1) in three dose cohorts. All 115 subjects initially received Noxafil injection for at least 7 days, and 63 subjects were transitioned to Noxafil PowderMix for delayed-release oral suspension. The mean overall treatment duration for all treated subjects was 20.6 days with 14.3 days (range: 1 to 28 days) on Noxafil injection and 11.6 days (range: 2 to 18 days) on Noxafil PowderMix for delayed-release oral suspension.

Reported adverse reaction profile of Noxafil in pediatric patients was consistent with the safety profile of Noxafil in adults.

6.2 Postmarketing Experience

The following adverse reaction has been identified during the post-approval use of posaconazole. Because these reactions are reported voluntarily from a population of uncertain size, it is not always possible to reliably estimate their frequency.

Endocrine Disorders: Pseudoaldosteronism

7 DRUG INTERACTIONS

Posaconazole is primarily metabolized via UDP glucuronosyltransferase and is a substrate of p-glycoprotein (P-gp) efflux. Therefore, inhibitors or inducers of these clearance pathways may affect posaconazole plasma concentrations. Coadministration of drugs that can decrease the plasma concentrations of posaconazole should generally be avoided unless the benefit outweighs the risk. If such drugs are necessary, patients should be monitored closely for breakthrough fungal infections.

Posaconazole is also a strong inhibitor of CYP3A4. Therefore, plasma concentrations of drugs predominantly metabolized by CYP3A4 may be increased by posaconazole [see Clinical Pharmacology (12.3)].

The following information was derived from data with Noxafil oral suspension or early tablet formulation unless otherwise noted. All drug interactions with Posaconazole oral suspension, except for those that affect the absorption of posaconazole (via gastric pH and motility), are considered relevant to Posaconazole injection, Posaconazole delayed-release tablet, and Posaconazole PowderMix for delayed-release oral suspension as well [see Drug Interactions (7.9) and (7.13)].

7.1 Immunosuppressants Metabolized by CYP3A4

Sirolimus: Concomitant administration of posaconazole with sirolimus increases the sirolimus blood concentrations by approximately 9-fold and can result in sirolimus toxicity. Therefore, posaconazole is contraindicated with sirolimus [see Contraindications (4.2) and Clinical Pharmacology (12.3)].

Tacrolimus: Posaconazole has been shown to significantly increase the Cmax and AUC of tacrolimus. At initiation of posaconazole treatment, reduce the tacrolimus dose to approximately one-third of the original dose. Frequent monitoring of tacrolimus whole blood trough concentrations should be performed during and at discontinuation of posaconazole treatment and the tacrolimus dose adjusted accordingly [see Warnings and Precautions (5.1) and Clinical Pharmacology (12.3)].

Cyclosporine: Posaconazole has been shown to increase cyclosporine whole blood concentrations in heart transplant patients upon initiation of posaconazole treatment. It is recommended to reduce cyclosporine dose to approximately three-fourths of the original dose upon initiation of posaconazole treatment. Frequent monitoring of cyclosporine whole blood trough concentrations should be performed during and at discontinuation of posaconazole treatment and the cyclosporine dose adjusted accordingly [see Warnings and Precautions (5.1) and Clinical Pharmacology (12.3)].

7.2 CYP3A4 Substrates

Concomitant administration of posaconazole with CYP3A4 substrates such as pimozide and quinidine may result in increased plasma concentrations of these drugs, leading to QTc prolongation and cases of torsades de pointes. Therefore, posaconazole is contraindicated with these drugs [see Contraindications (4.3) and Warnings and Precautions (5.2)].

7.3 HMG-CoA Reductase Inhibitors (Statins) Primarily Metabolized Through CYP3A4

Concomitant administration of posaconazole with simvastatin increases the simvastatin plasma concentrations by approximately 10-fold. Therefore, posaconazole is contraindicated with HMG-CoA reductase inhibitors primarily metabolized through CYP3A4 [see Contraindications (4.4) and Clinical Pharmacology (12.3)].

7.4 Ergot Alkaloids

Most of the ergot alkaloids are substrates of CYP3A4. Posaconazole may increase the plasma concentrations of ergot alkaloids (ergotamine and dihydroergotamine) which may lead to ergotism. Therefore, posaconazole is contraindicated with ergot alkaloids [see Contraindications (4.5)].

7.5 Benzodiazepines Metabolized by CYP3A4

Concomitant administration of posaconazole with midazolam increases the midazolam plasma concentrations by approximately 5-fold. Increased plasma midazolam concentrations could potentiate and prolong hypnotic and sedative effects. Concomitant use of posaconazole and other benzodiazepines metabolized by CYP3A4 (e.g., alprazolam, triazolam) could result in increased plasma concentrations of these benzodiazepines. Patients must be monitored closely for adverse effects associated with high plasma concentrations of benzodiazepines metabolized by CYP3A4 and benzodiazepine receptor antagonists must be available to reverse these effects [see Warnings and Precautions (5.7) and Clinical Pharmacology (12.3)].

7.6 Anti-HIV Drugs

Efavirenz: Efavirenz induces UDP-glucuronidase and significantly decreases posaconazole plasma concentrations [see Clinical Pharmacology (12.3)]. It is recommended to avoid concomitant use of efavirenz with posaconazole unless the benefit outweighs the risks.

Ritonavir and Atazanavir: Ritonavir and atazanavir are metabolized by CYP3A4 and posaconazole increases plasma concentrations of these drugs [see Clinical Pharmacology (12.3)]. Frequent monitoring of adverse effects and toxicity of ritonavir and atazanavir should be performed during coadministration with posaconazole.

Fosamprenavir: Combining fosamprenavir with posaconazole may lead to decreased posaconazole plasma concentrations. If concomitant administration is required, close monitoring for breakthrough fungal infections is recommended [see Clinical Pharmacology (12.3)].

7.7 Rifabutin

Rifabutin induces UDP-glucuronidase and decreases posaconazole plasma concentrations. Rifabutin is also metabolized by CYP3A4. Therefore, coadministration of rifabutin with posaconazole increases rifabutin plasma concentrations [see Clinical Pharmacology (12.3)]. Concomitant use of posaconazole and rifabutin should be avoided unless the benefit to the patient outweighs the risk. However, if concomitant administration is required, close monitoring for breakthrough fungal infections as well as frequent monitoring of full blood counts and adverse reactions due to increased rifabutin plasma concentrations (e.g., uveitis, leukopenia) are recommended.

7.8 Phenytoin

Phenytoin induces UDP-glucuronidase and decreases posaconazole plasma concentrations. Phenytoin is also metabolized by CYP3A4. Therefore, coadministration of phenytoin with posaconazole increases phenytoin plasma concentrations [see Clinical Pharmacology (12.3)]. Concomitant use of posaconazole and phenytoin should be avoided unless the benefit to the patient outweighs the risk. However, if concomitant administration is required, close monitoring for breakthrough fungal infections is recommended and frequent monitoring of phenytoin concentrations should be performed while coadministered with posaconazole and dose reduction of phenytoin should be considered.

7.9 Gastric Acid Suppressors/Neutralizers

Posaconazole Delayed-Release Tablet:

No clinically relevant effects on the pharmacokinetics of posaconazole were observed when Posaconazole delayed-release tablets are concomitantly used with antacids, H2-receptor antagonists and proton pump inhibitors [see Clinical Pharmacology (12.3)]. No dosage adjustment of Posaconazole delayed-release tablets is required when Posaconazole delayed-release tablets are concomitantly used with antacids, H2-receptor antagonists and proton pump inhibitors.

Posaconazole Oral Suspension:

Cimetidine (an H2-receptor antagonist) and esomeprazole (a proton pump inhibitor) when given with Posaconazole oral suspension results in decreased posaconazole plasma concentrations [see Clinical Pharmacology (12.3)]. It is recommended to avoid concomitant use of cimetidine and esomeprazole with Posaconazole oral suspension unless the benefit outweighs the risks. However, if concomitant administration is required, close monitoring for breakthrough fungal infections is recommended.

No clinically relevant effects were observed when Posaconazole oral suspension is concomitantly used with antacids and H2-receptor antagonists other than cimetidine. No dosage adjustment of Posaconazole oral suspension is required when Posaconazole oral suspension is concomitantly used with antacids and H2-receptor antagonists other than cimetidine.

7.10 Vinca Alkaloids

Most of the vinca alkaloids (e.g., vincristine and vinblastine) are substrates of CYP3A4. Concomitant administration of azole antifungals, including posaconazole, with vincristine has been associated with serious adverse reactions [see Warnings and Precautions (5.8)]. Posaconazole may increase the plasma concentrations of vinca alkaloids which may lead to neurotoxicity and other serious adverse reactions. Therefore, reserve azole antifungals, including posaconazole, for patients receiving a vinca alkaloid, including vincristine, who have no alternative antifungal treatment options.

7.11 Calcium Channel Blockers Metabolized by CYP3A4

Posaconazole may increase the plasma concentrations of calcium channel blockers metabolized by CYP3A4 (e.g., verapamil, diltiazem, nifedipine, nicardipine, felodipine). Frequent monitoring for adverse reactions and toxicity related to calcium channel blockers is recommended during coadministration. Dose reduction of calcium channel blockers may be needed.

7.12 Digoxin

Increased plasma concentrations of digoxin have been reported in patients receiving digoxin and posaconazole. Therefore, monitoring of digoxin plasma concentrations is recommended during coadministration.

7.13 Gastrointestinal Motility Agents

Posaconazole Delayed-Release Tablet:

Concomitant administration of metoclopramide with Posaconazole delayed-release tablets did not affect the pharmacokinetics of posaconazole [see Clinical Pharmacology (12.3)]. No dosage adjustment of Posaconazole delayed-release tablets is required when given concomitantly with metoclopramide.

Posaconazole Oral Suspension:

Metoclopramide, when given with Posaconazole oral suspension, decreases posaconazole plasma concentrations [see Clinical Pharmacology (12.3)]. If metoclopramide is concomitantly administered with Posaconazole oral suspension, it is recommended to closely monitor for breakthrough fungal infections.

Loperamide does not affect posaconazole plasma concentrations after Posaconazole oral suspension administration [see Clinical Pharmacology (12.3)]. No dosage adjustment of Posaconazole oral suspension is required when loperamide and Posaconazole oral suspension are used concomitantly.

7.14 Glipizide

Although no dosage adjustment of glipizide is required, it is recommended to monitor glucose concentrations when posaconazole and glipizide are concomitantly used.

7.15 Venetoclax

Concomitant use of venetoclax (a CYP3A4 substrate) with posaconazole increases venetoclax Cmax and AUC0-INF, which may increase venetoclax toxicities [see Contraindications (4.6), Warnings and Precautions (5.10)]. Refer to the venetoclax prescribing information for more information on the dosing instructions and the extent of increase in venetoclax exposure.

8 USE IN SPECIFIC POPULATIONS

8.1 Pregnancy

Risk Summary

Based on findings from animal data, posaconazole may cause fetal harm when administered to pregnant women. Available data for use of Noxafil in pregnant women are insufficient to establish a drug-associated risk of major birth defects, miscarriage, or adverse maternal or fetal outcomes. In animal reproduction studies, skeletal malformations (cranial malformations and missing ribs) and maternal toxicity (reduced food consumption and reduced body weight gain) were observed when posaconazole was dosed orally to pregnant rats during organogenesis at doses ≥1.4 times the 400 mg twice daily oral suspension regimen based on steady-state plasma concentrations of Noxafil in healthy volunteers. In pregnant rabbits dosed orally during organogenesis, increased resorptions, reduced litter size, and reduced body weight gain of females were seen at doses 5 times the exposure achieved with the 400 mg twice daily oral suspension regimen. Doses of ≥ 3 times the clinical exposure caused an increase in resorptions in these rabbits (see Data). Based on animal data, advise pregnant women of the potential risk to a fetus.

The estimated background risk of major birth defects and miscarriage for the indicated population is unknown. All pregnancies have a background risk of birth defect, loss, or other adverse outcomes. In the U.S. general population, the estimated background risk of major birth defects and miscarriage in clinically recognized pregnancies is 2 to 4% and 15 to 20%, respectively.

Data

Animal Data

Posaconazole resulted in maternal toxicity (reduced food consumption and reduced body weight gain) and skeletal malformations (cranial malformations and missing ribs) when given orally to pregnant rats during organogenesis (Gestational Days 6 through 15) at doses ≥27 mg/kg (≥1.4 times the 400 mg twice daily oral suspension regimen based on steady-state plasma concentrations of drug in healthy volunteers). The no-effect dose for malformations and maternal toxicity in rats was 9 mg/kg, which is 0.7 times the exposure achieved with the 400 mg twice daily oral suspension regimen. No malformations were seen in rabbits dosed during organogenesis (Gestational Days 7 through 19) at doses up to 80 mg/kg (5 times the exposure achieved with the 400 mg twice daily oral suspension regimen). In the rabbit, the no-effect dose was 20 mg/kg, while high doses of 40 mg/kg and 80 mg/kg (3 or 5 times the clinical exposure) caused an increase in resorptions. In rabbits dosed at 80 mg/kg, a reduction in body weight gain of females and a reduction in litter size were seen.

8.2 Lactation

Risk Summary

There are no data on the presence of posaconazole in human milk, the effects on the breastfed infant, or the effects on milk production. Posaconazole is excreted in the milk of lactating rats. When a drug is present in animal milk, it is likely that the drug will be present in human milk. The developmental and health benefits of breastfeeding should be considered along with the mother's clinical need for posaconazole and any potential adverse effects on the breastfed child from posaconazole or from the underlying maternal condition.

8.4 Pediatric Use

The safety and effectiveness of Posaconazole oral suspension and Posaconazole delayed-release tablets for the prophylaxis of invasive Aspergillus and Candida infections have been established in pediatric patients aged 2 and older who are at high risk of developing these infections due to being severely immunocompromised, such as HSCT recipients with GVHD or those with hematologic malignancies with prolonged neutropenia from chemotherapy.

The safety and effectiveness of Posaconazole injection and Posaconazole delayed-release tablets for the treatment of invasive aspergillosis have been established in pediatric patients aged 13 years and older.

The safety and effectiveness of Posaconazole oral suspension have been established for the treatment of oropharyngeal candidiasis (OPC), including OPC refractory (rOPC) to itraconazole and/or fluconazole in pediatric patients aged 13 years and older.

Use of posaconazole in these age groups is supported by evidence from adequate and well-controlled studies of Noxafil in adult and pediatric patients and additional pharmacokinetic and safety data in pediatric patients 2 years of age and older [see Adverse Reactions (6.1), Clinical Pharmacology (12.3), and Clinical Studies (14)]. The safety and effectiveness of posaconazole have not been established in pediatric patients younger than 2 years of age.

8.5 Geriatric Use

No overall differences in the safety of Noxafil delayed-release tablets and Noxafil oral suspension were observed between geriatric patients and younger adult patients in the clinical trials; therefore, no dosage adjustment is recommended for any formulation of posaconazole in geriatric patients. No clinically meaningful differences in the pharmacokinetics of Noxafil were observed in geriatric patients compared to younger adult patients during clinical trials [see Clinical Pharmacology (12.3)].

Of the 230 patients treated with Noxafil delayed-release tablets, 38 (17%) were greater than 65 years of age.

Of the 605 patients randomized to Noxafil oral suspension in Noxafil Oral Suspension Study 1 and Study 2, 63 (10%) were ≥65 years of age. In addition, 48 patients treated with greater than or equal to 800-mg/day Noxafil oral suspension in another indication were ≥65 years of age. Of the 288 patients randomized to Noxafil injection/Noxafil delayed-release tablets in the Aspergillosis Treatment Study, 85 (29%) were ≥65 years of age.

No overall differences in the pharmacokinetics and safety were observed between elderly and young subjects during clinical trials, but greater sensitivity of some older individuals cannot be ruled out.

8.6 Renal Impairment

Following single-dose administration of 400 mg of the Noxafil oral suspension, there was no significant effect of mild (eGFR: 50-80 mL/min/1.73 m^2, n=6) or moderate (eGFR: 20-49 mL/min/1.73 m^2, n=6) renal impairment on posaconazole pharmacokinetics; therefore, no dose adjustment is required in patients with mild to moderate renal impairment. In subjects with severe renal impairment (eGFR: <20 mL/min/1.73 m^2), the mean plasma exposure (AUC) was similar to that in patients with normal renal function (eGFR: >80 mL/min/1.73 m^2); however, the range of the AUC estimates was highly variable (CV=96%) in these subjects with severe renal impairment as compared to that in the other renal impairment groups (CV<40%). Due to the variability in exposure, patients with severe renal impairment should be monitored closely for breakthrough fungal infections [see Dosage and Administration (2)]. Similar recommendations apply to Posaconazole delayed-release tablets; however, a specific study has not been conducted with the Posaconazole delayed-release tablets.

8.7 Hepatic Impairment

After a single oral dose of Noxafil oral suspension 400 mg, the mean AUC was 43%, 27%, and 21% higher in subjects with mild (Child-Pugh Class A, N=6), moderate (Child-Pugh Class B, N=6), or severe (Child-Pugh Class C, N=6) hepatic impairment, respectively, compared to subjects with normal hepatic function (N=18). Compared to subjects with normal hepatic function, the mean Cmax was 1% higher, 40% higher, and 34% lower in subjects with mild, moderate, or severe hepatic impairment, respectively. The mean apparent oral clearance (CL/F) was reduced by 18%, 36%, and 28% in subjects with mild, moderate, or severe hepatic impairment, respectively, compared to subjects with normal hepatic function. The elimination half-life (t½) was 27 hours, 39 hours, 27 hours, and 43 hours in subjects with normal hepatic function and mild, moderate, or severe hepatic impairment, respectively.

It is recommended that no dose adjustment of posaconazole is needed in patients with mild to severe hepatic impairment (Child-Pugh Class A, B, or C) [see Dosage and Administration (2) and Warnings and Precautions (5.5)]. Similar recommendations apply to Posaconazole delayed-release tablets; however, a specific study has not been conducted with the Posaconazole delayed-release tablets.

8.8 Gender

The pharmacokinetics of posaconazole are comparable in males and females. No adjustment in the dosage of posaconazole is necessary based on gender.

8.9 Race

The pharmacokinetic profile of posaconazole is not significantly affected by race. No adjustment in the dosage of posaconazole is necessary based on race.

8.10 Weight

Pharmacokinetic modeling suggests that patients weighing greater than 120 kg may have lower posaconazole plasma drug exposure. It is, therefore, suggested to closely monitor for breakthrough fungal infections particularly when using Posaconazole oral suspension [see Clinical Pharmacology (12.3)].

10 OVERDOSAGE

There is no experience with overdosage of Posaconazole delayed-release tablets.

During the clinical trials, some patients received Noxafil oral suspension up to 1600 mg/day with no adverse reactions noted that were different from the lower doses. In addition, accidental overdose was noted in one patient who took 1200 mg twice daily Noxafil oral suspension for 3 days. No related adverse reactions were noted by the investigator.

Posaconazole is not removed by hemodialysis.

11 DESCRIPTION

Posaconazole is an azole antifungal agent available as delayed-release tablet or suspension for oral administration.

Posaconazole is designated chemically as 4-[4-[4-[4-[[ (3R,5R)-5- (2,4-difluorophenyl)tetrahydro-5- (1H-1,2,4-triazol-1-ylmethyl)-3-furanyl]methoxy]phenyl]-1-piperazinyl]phenyl]-2-[(1S,2S)-1-ethyl-2-hydroxypropyl]-2,4-dihydro-3H-1,2,4-triazol-3-one with an empirical formula of C37H42F2N8O4 and a molecular weight of 700.8. The chemical structure is:

Posaconazole Delayed-Release Tablets

Posaconazole is a white powder with a low aqueous solubility.

Posaconazole delayed-release tablet is a yellow, coated, oblong tablet containing 100 mg of posaconazole. Each delayed-release tablet contains the inactive ingredients: croscarmellose sodium, hydroxypropylcellulose, hypromellose acetate succinate, iron oxide yellow, Macrogol/PEG 3350, magnesium stearate, microcrystalline cellulose, polyvinyl alcohol partially hydrolyzed, silicon dioxide, talc, and titanium dioxide.

Posaconazole Oral Suspension

Posaconazole oral suspension is a white, cherry-flavored immediate-release suspension containing 40 mg of posaconazole per mL and the following inactive ingredients: artificial cherry flavor, citric acid monohydrate, glycerin, liquid glucose, polysorbate 80, purified water, simethicone, sodium benzoate, sodium citrate dihydrate, titanium dioxide, and xanthan gum.

12 CLINICAL PHARMACOLOGY

12.1 Mechanism of Action

Posaconazole is an azole antifungal agent [see Clinical Pharmacology (12.4)].

12.2 Pharmacodynamics

Exposure Response Relationship Prophylaxis: In clinical studies of neutropenic patients who were receiving cytotoxic chemotherapy for acute myelogenous leukemia (AML) or myelodysplastic syndromes (MDS) or hematopoietic stem cell transplant (HSCT) recipients with Graft versus Host Disease (GVHD), a wide range of plasma exposures to posaconazole was noted following administration of Noxafil oral suspension. A pharmacokinetic-pharmacodynamic analysis of patient data revealed an apparent association between average posaconazole concentrations (Cavg) and prophylactic efficacy (Table 11). A lower Cavg may be associated with an increased risk of treatment failure, defined as treatment discontinuation, use of empiric systemic antifungal therapy (SAF), or occurrence of breakthrough invasive fungal infections.

Table 11: Noxafil Oral Suspension Exposure Analysis (Cavg) in Prophylaxis Trials
 | Prophylaxis in AML/MDS [Neutropenic patients who were receiving cytotoxic chemotherapy for AML or MDS] |  | Prophylaxis in GVHD [HSCT recipients with GVHD]
 | Cavg Range (ng/mL) | Treatment Failure [Defined as treatment discontinuation, use of empiric systemic antifungal therapy (SAF), or occurrence of breakthrough invasive fungal infections] (%) | Cavg Range (ng/mL) | Treatment Failure (%)
Quartile 1 | 90-322 | 54.7 | 22-557 | 44.4
Quartile 2 | 322-490 | 37.0 | 557-915 | 20.6
Quartile 3 | 490-734 | 46.8 | 915-1563 | 17.5
Quartile 4 | 734-2200 | 27.8 | 1563-3650 | 17.5
Cavg = the average posaconazole concentration when measured at steady state

Exposure Response Relationship Treatment of Invasive Aspergillosis:

Across a range of posaconazole plasma minimum concentrations (Cmin, range: 244 to 5663 ng/mL) following administration of Noxafil injection and Noxafil delayed-release tablets in patients treated for invasive aspergillosis in Aspergillosis Treatment Study, there was no association between posaconazole Cmin and treatment efficacy [see Clinical Pharmacology (12.3) and Clinical Studies (14.1)]. Similarly, across a range of population pharmacokinetic model-predicted steady-state plasma average concentrations (Cavg, range: 589 to 6315 ng/mL), there was no association between posaconazole Cavg and treatment efficacy.

12.3 Pharmacokinetics

General Pharmacokinetic Characteristics

Posaconazole Delayed-Release Tablets

Noxafil delayed-release tablets exhibit dose proportional pharmacokinetics after single and multiple dosing up to 300 mg. The mean pharmacokinetic parameters of posaconazole at steady state following administration of Noxafil delayed-release tablets 300 mg twice daily on Day 1, then 300 mg once daily thereafter in healthy volunteers and in neutropenic patients who are receiving cytotoxic chemotherapy for AML or MDS or HSCT recipients with GVHD are shown in Table 12.

Table 12: Arithmetic Mean (%CV) of Steady State PK Parameters in Healthy Volunteers and Patients Following Administration of Noxafil Delayed-Release Tablets (300 mg) [300 mg twice daily on Day 1, then 300 mg once daily thereafter]
 | N | AUC0-24 hr (ng∙hr/mL) | Cav [Cav = time-averaged concentrations (i.e., AUC0-24 hr/24hr)] (ng/mL) | Cmax (ng/mL) | Cmin (ng/mL) | Tmax [Median (minimum-maximum)] (hr) | t1/2 (hr) | CL/F (L/hr)
Healthy Volunteers | 12 | 51618 (25) | 2151 (25) | 2764 (21) | 1785 (29) | 4 (3-6) | 31 (40) | 7.5 (26)
Patients | 50 | 37900 (42) | 1580 (42) | 2090 (38) | 1310 (50) | 4 (1.3-8.3) | - | 9.39 (45)
CV = coefficient of variation expressed as a percentage (%CV); AUC0-T = Area under the plasma concentration-time curve from time zero to 24 hr; Cmax = maximum observed concentration; Cmin = minimum observed plasma concentration; Tmax = time of maximum observed concentration; t½ = terminal phase half-life; CL/F = Apparent total body clearance

Posaconazole Oral Suspension

Dose-proportional increases in plasma exposure (AUC) to Noxafil oral suspension were observed following single oral doses from 50 mg to 800 mg and following multiple-dose administration from 50 mg twice daily to 400 mg twice daily in healthy volunteers. No further increases in exposure were observed when the dose of the oral suspension increased from 400 mg twice daily to 600 mg twice daily in febrile neutropenic patients or those with refractory invasive fungal infections.

The mean (%CV) [min-max] Noxafil oral suspension average steady-state plasma concentrations (Cavg) and steady-state pharmacokinetic parameters in patients following administration of 200 mg three times a day and 400 mg twice daily of the oral suspension are provided in Table 13.

Table 13: The Mean (%CV) [min-max] Posaconazole Steady-State Pharmacokinetic Parameters in Patients Following Oral Administration of Noxafil Oral Suspension 200 mg Three Times a Day and 400 mg Twice Daily
Dose [Oral suspension administration] | Cavg (ng/mL) | AUC [AUC (0-24 hr) for 200 mg three times a day and AUC (0-12 hr) for 400 mg twice daily] (ng∙hr/mL) | CL/F (L/hr) | V/F (L) | t½ (hr)
200 mg three times a day [HSCT recipients with GVHD] (n=252) | 1103 (67) [21.5-3650] | ND [Not done] | ND | ND | ND
200 mg three times a day [Neutropenic patients who were receiving cytotoxic chemotherapy for acute myelogenous leukemia or myelodysplastic syndromes] (n=215) | 583 (65) [89.7-2200] | 15,900 (62) [4100-56,100] | 51.2 (54) [10.7-146] | 2425 (39) [828-5702] | 37.2 (39) [19.1-148]
400 mg twice daily [Febrile neutropenic patients or patients with refractory invasive fungal infections, Cavg n=24 The variability in average plasma posaconazole concentrations in patients was relatively higher than that in healthy subjects.] (n=23) | 723 (86) [6.70-2256] | 9093 (80) [1564-26,794] | 76.1 (78) [14.9-256] | 3088 (84) [407-13,140] | 31.7 (42) [12.4-67.3]
Cavg = the average posaconazole concentration when measured at steady state

Absorption:

Posaconazole Delayed-Release Tablets

When given orally in healthy volunteers, Noxafil delayed-release tablets are absorbed with a median Tmax of 4 to 5 hours. Steady-state plasma concentrations are attained by Day 6 at the 300 mg dose (once daily after twice daily loading dose at Day 1). The absolute bioavailability of the oral delayed-release tablet is approximately 54% under fasted conditions. The Cmax and AUC of posaconazole following administration of Noxafil delayed-release tablets is increased 16% and 51%, respectively, when given with a high fat meal compared to a fasted state (see Table 14).

Table 14: Statistical Comparison of Plasma Pharmacokinetics of Posaconazole Following Single Oral Dose Administration of 300 mg Noxafil Delayed-Release Tablet to Healthy Subjects under Fasting and Fed Conditions
 | Fasting Conditions |  | Fed Conditions (High Fat Meal) [48.5 g fat] |  | Fed/Fasting
Pharmacokinetic Parameter | N | Mean (%CV) | N | Mean (%CV) | GMR (90% CI)
Cmax (ng/mL) | 14 | 935 (34) | 16 | 1060 (25) | 1.16 (0.96, 1.41)
AUC0-72hr (hr∙ng/mL) | 14 | 26200 (28) | 16 | 38400 (18) | 1.51 (1.33, 1.72)
Tmax [Median (Min, Max) reported for Tmax] (hr) | 14 | 5.00 (3.00, 8.00) | 16 | 6.00 (5.00, 24.00) | N/A
GMR=Geometric least-squares mean ratio; CI=Confidence interval

Concomitant administration of Noxafil delayed-release tablets with drugs affecting gastric pH or gastric motility did not demonstrate any significant effects on posaconazole pharmacokinetic exposure (see Table 15).

Table 15: The Effect of Concomitant Medications that Affect the Gastric pH and Gastric Motility on the Pharmacokinetics of Noxafil Delayed-Release Tablets in Healthy Volunteers
Coadministered Drug | Administration Arms | Change in Cmax (ratio estimate [Ratio Estimate is the ratio of coadministered drug plus Noxafil to Noxafil alone for Cmax or AUC0-last.] ; 90% CI of the ratio estimate) | Change in AUC0-last (ratio estimate; 90% CI of the ratio estimate)
Mylanta® Ultimate strength liquid (Increase in gastric pH) | 25.4 mEq/5 mL, 20 mL | ↑6% (1.06; 0.90 -1.26)↑ | ↑4% (1.04; 0.90 -1.20)
Ranitidine (Zantac®) (Alteration in gastric pH) | 150 mg (morning dose of 150 mg Ranitidine twice daily) | ↑4% (1.04; 0.88 -1.23)↑ | ↓3% (0.97; 0.84 -1.12)
Esomeprazole (Nexium®) (Increase in gastric pH) | 40 mg (every morning for 5 days, Day -4 to 1) | ↑2% (1.02; 0.88-1.17)↑ | ↑5% (1.05; 0.89 -1.24)
Metoclopramide (Reglan®) (Increase in gastric motility) | 15 mg four times daily for 2 days (Day -1 and 1) | ↓14% (0.86, 0.73,1.02) | ↓7% (0.93, 0.803,1.07)

Posaconazole Oral Suspension

Noxafil oral suspension is absorbed with a median Tmax of ~3 to 5 hours. Steady-state plasma concentrations are attained at 7 to 10 days following multiple-dose administration.

Following single-dose administration of 200 mg, the mean AUC and Cmax of posaconazole are approximately 3-times higher when the oral suspension is administered with a nonfat meal and approximately 4-times higher when administered with a high-fat meal (~50 gm fat) relative to the fasted state. Following single-dose administration of Noxafil oral suspension 400 mg, the mean AUC and Cmax of posaconazole are approximately 3-times higher when administered with a liquid nutritional supplement (14 gm fat) relative to the fasted state (see Table 16). In addition, the effects of varying gastric administration conditions on the Cmax and AUC of Noxafil oral suspension in healthy volunteers have been investigated and are shown in Table 17.

In order to assure attainment of adequate plasma concentrations, it is recommended to administer Posaconazole oral suspension during or immediately following a full meal. In patients who cannot eat a full meal, Posaconazole oral suspension should be taken with a liquid nutritional supplement or an acidic carbonated beverage (e.g., ginger ale).

Table 16: The Mean (%CV) [min-max] Posaconazole Pharmacokinetic Parameters Following Single-Dose Noxafil Oral Suspension Administration of 200 mg and 400 mg Under Fed and Fasted Conditions
Dose (mg) | Cmax (ng/mL) | Tmax [Median [min-max].] (hr) | AUC (I) (ng∙hr/mL) | CL/F (L/hr) | t½ (hr)
200 mg fasted (n=20) [n=15 for AUC (I), CL/F, and t½] | 132 (50) [45-267] | 3.50 [1.5-36 [The subject with Tmax of 36 hrs had relatively constant plasma levels over 36 hrs (1.7 ng/mL difference between 4 hrs and 36 hrs).] ] | 4179 (31) [2705-7269] | 51 (25) [28-74] | 23.5 (25) [15.3-33.7]
200 mg nonfat (n=20) | 378 (43) [131-834] | 4 [3-5] | 10,753 (35) [4579-17,092] | 21 (39) [12-44] | 22.2 (18) [17.4-28.7]
200 mg high fat (54 gm fat) (n=20) | 512 (34) [241-1016] | 5 [4-5] | 15,059 (26) [10,341-24,476] | 14 (24) [8.2-19] | 23.0 (19) [17.2-33.4]
400 mg fasted (n=23) [n=10 for AUC (I), CL/F, and t½] | 121 (75) [27-366] | 4 [2-12] | 5258 (48) [2834-9567] | 91 (40) [42-141] | 27.3 (26) [16.8-38.9]
400 mg with liquid nutritional supplement (14 gm fat) (n=23) | 355 (43) [145-720] | 5 [4-8] | 11,295 (40) [3865-20,592] | 43 (56) [19-103] | 26.0 (19) [18.2-35.0]

Table 17: The Effect of Varying Gastric Administration Conditions on the Cmax and AUC of Noxafil Oral Suspension in Healthy Volunteers [In 5 subjects, the Cmax and AUC decreased substantially (range: -27% to -53% and -33% to -51%, respectively) when Noxafil was administered via an NG tube compared to when Noxafil was administered orally. It is recommended to closely monitor patients for breakthrough fungal infections when posaconazole is administered via an NG tube because a lower plasma exposure may be associated with an increased risk of treatment failure.]
Study Description | Administration Arms | Change in Cmax (ratio estimate [Ratio Estimate is the ratio of coadministered drug plus Noxafil to coadministered drug alone for Cmax or AUC.] ; 90% CI of the ratio estimate) | Change in AUC (ratio estimate; 90% CI of the ratio estimate)
400-mg single dose with a high-fat meal relative to fasted state (n=12) | 5 minutes before high-fat meal | ↑96% (1.96; 1.48-2.59) | ↑111% (2.11; 1.60-2.78)
400-mg single dose with a high-fat meal relative to fasted state (n=12) | During high-fat meal | ↑339% (4.39; 3.32-5.80) | ↑382% (4.82; 3.66-6.35)
400-mg single dose with a high-fat meal relative to fasted state (n=12) | 20 minutes after high-fat meal | ↑333% (4.33; 3.28-5.73) | ↑387% (4.87; 3.70-6.42)
400 mg twice daily and 200 mg four times daily for 7 days in fasted state and with liquid nutritional supplement (BOOST®) (n=12) | 400 mg twice daily with BOOST | ↑65% (1.65; 1.29-2.11) | ↑66% (1.66; 1.30-2.13)
400 mg twice daily and 200 mg four times daily for 7 days in fasted state and with liquid nutritional supplement (BOOST®) (n=12) | 200 mg four times daily with BOOST | No Effect | No Effect
Divided daily dose from 400 mg twice daily to 200 mg four times daily for 7 days regardless of fasted conditions or with BOOST (n=12) | Fasted state | ↑136% (2.36; 1.84-3.02) | ↑161% (2.61; 2.04-3.35)
Divided daily dose from 400 mg twice daily to 200 mg four times daily for 7 days regardless of fasted conditions or with BOOST (n=12) | With BOOST | ↑137% (2.37; 1.86-3.04) | ↑157% (2.57; 2.00-3.30)
400-mg single dose with carbonated acidic beverage (ginger ale) and/or proton pump inhibitor (esomeprazole) (n=12) | Ginger ale | ↑92% (1.92; 1.51-2.44) | ↑70% (1.70; 1.43-2.03)
400-mg single dose with carbonated acidic beverage (ginger ale) and/or proton pump inhibitor (esomeprazole) (n=12) | Esomeprazole | ↓32% (0.68; 0.53-0.86) | ↓30% (0.70; 0.59-0.83)
400-mg single dose with a prokinetic agent (metoclopramide 10 mg three times a day for 2 days) + BOOST or an antikinetic agent (loperamide 4-mg single dose) + BOOST (n=12) | With metoclopramide + BOOST | ↓21% (0.79; 0.72-0.87) | ↓19% (0.81; 0.72-0.91)
400-mg single dose with a prokinetic agent (metoclopramide 10 mg three times a day for 2 days) + BOOST or an antikinetic agent (loperamide 4-mg single dose) + BOOST (n=12) | With loperamide + BOOST | ↓3% (0.97; 0.88-1.07) | ↑11% (1.11; 0.99-1.25)
400-mg single dose either orally with BOOST or via an NG tube with BOOST (n=16) | Via NG tube [NG = nasogastric] | ↓19% (0.81; 0.71-0.91) | ↓23% (0.77; 0.69-0.86)

Concomitant administration of Noxafil oral suspension with drugs affecting gastric pH or gastric motility results in lower posaconazole exposure. (See Table 18.)

Table 18: The Effect of Concomitant Medications that Affect the Gastric pH and Gastric Motility on the Pharmacokinetics of Noxafil Oral Suspension in Healthy Volunteers
Coadministered Drug (Postulated Mechanism of Interaction) | Coadministered Drug Dose/Schedule | Noxafil Dose/Schedule | Effect on Bioavailability of Posaconazole
Coadministered Drug (Postulated Mechanism of Interaction) | Coadministered Drug Dose/Schedule | Noxafil Dose/Schedule | Change in Mean Cmax (ratio estimate [Ratio Estimate is the ratio of coadministered drug plus Noxafil to coadministered drug alone for Cmax or AUC.] ; 90% CI of the ratio estimate) | Change in Mean AUC (ratio estimate; 90% CI of the ratio estimate)
Cimetidine (Alteration of gastric pH) | 400 mg twice daily × 10 days | 200 mg (tablets) once daily × 10 days [The tablet refers to a non-commercial tablet formulation without polymer.] | ↓ 39% (0.61; 0.53-0.70) | ↓ 39% (0.61; 0.54-0.69)
Esomeprazole (Increase in gastric pH) [The drug interactions associated with the oral suspension are also relevant for the delayed-release tablet with the exception of Esomeprazole and Metoclopramide.] | 40 mg every morning × 3 days | 400 mg (oral suspension) single dose | ↓ 46% (0.54; 0.43-0.69) | ↓ 32% (0.68; 0.57-0.81)
Metoclopramide (Increase in gastric motility) | 10 mg three times a day × 2 days | 400 mg (oral suspension) single dose | ↓ 21% (0.79; 0.72-0.87) | ↓ 19% (0.81; 0.72-0.91)

Distribution:

Posaconazole is highly bound to human plasma proteins (>98%), predominantly to albumin.

Metabolism:

Posaconazole primarily circulates as the parent compound in plasma. Of the circulating metabolites, the majority are glucuronide conjugates formed via UDP glucuronidation (phase 2 enzymes). Posaconazole does not have any major circulating oxidative (CYP450 mediated) metabolites. The excreted metabolites in urine and feces account for ~17% of the administered radiolabeled dose.

Posaconazole is primarily metabolized via UDP glucuronidation (phase 2 enzymes) and is a substrate for p-glycoprotein (P-gp) efflux. Therefore, inhibitors or inducers of these clearance pathways may affect posaconazole plasma concentrations. A summary of drugs studied clinically with the oral suspension or an early tablet formulation, which affect posaconazole concentrations, is provided in Table 19.

Table 19: Summary of the Effect of Coadministered Drugs on Noxafil in Healthy Volunteers
Coadministered Drug (Postulated Mechanism of Interaction) | Coadministered Drug Dose/Schedule | Noxafil Dose/Schedule | Effect on Bioavailability of Posaconazole
Coadministered Drug (Postulated Mechanism of Interaction) | Coadministered Drug Dose/Schedule | Noxafil Dose/Schedule | Change in Mean Cmax (ratio estimate [Ratio Estimate is the ratio of coadministered drug plus Noxafil to Noxafil alone for Cmax or AUC.] ; 90% CI of the ratio estimate) | Change in Mean AUC (ratio estimate; 90% CI of the ratio estimate)
Efavirenz (UDP-G Induction) | 400 mg once daily × 10 and 20 days | 400 mg (oral suspension) twice daily × 10 and 20 days | ↓45% (0.55; 0.47-0.66) | ↓ 50% (0.50; 0.43-0.60)
Fosamprenavir (unknown mechanism) | 700 mg twice daily x 10 days | 200 mg once daily on the 1st day, 200 mg twice daily on the 2nd day, then 400 mg twice daily x 8 Days | ↓21% 0.79 (0.71-0.89) | ↓23% 0.77 (0.68-0.87)
Rifabutin (UDP-G Induction) | 300 mg once daily x 17 days | 200 mg (tablets) once daily × 10 days [The tablet refers to a non-commercial tablet formulation without polymer.] | ↓ 43% (0.57; 0.43-0.75) | ↓ 49% (0.51; 0.37-0.71)
Phenytoin (UDP-G Induction) | 200 mg once daily x 10 days | 200 mg (tablets) once daily × 10 days | ↓ 41% (0.59; 0.44-0.79) | ↓ 50% (0.50; 0.36-0.71)

In vitro studies with human hepatic microsomes and clinical studies indicate that posaconazole is an inhibitor primarily of CYP3A4. A clinical study in healthy volunteers also indicates that posaconazole is a strong CYP3A4 inhibitor as evidenced by a >5-fold increase in midazolam AUC. Therefore, plasma concentrations of drugs predominantly metabolized by CYP3A4 may be increased by posaconazole. A summary of the drugs studied clinically, for which plasma concentrations were affected by posaconazole, is provided in Table 20 [see Contraindications (4) and Drug Interactions (7.1) including recommendations].

Table 20: Summary of the Effect of Noxafil on Coadministered Drugs in Healthy Volunteers and Patients
Coadministered Drug (Postulated Mechanism of Interaction is Inhibition of CYP3A4 by Posaconazole) | Coadministered Drug Dose/Schedule | Noxafil Dose/Schedule | Effect on Bioavailability of Coadministered Drugs
Coadministered Drug (Postulated Mechanism of Interaction is Inhibition of CYP3A4 by Posaconazole) | Coadministered Drug Dose/Schedule | Noxafil Dose/Schedule | Change in Mean Cmax (ratio estimate [Ratio Estimate is the ratio of coadministered drug plus Noxafil to coadministered drug alone for Cmax or AUC.] ; 90% CI of the ratio estimate) | Change in Mean AUC (ratio estimate; 90% CI of the ratio estimate)
Sirolimus | 2-mg single oral dose | 400 mg (oral suspension) twice daily x 16 days | ↑ 572% (6.72; 5.62-8.03) | ↑ 788% (8.88; 7.26-10.9)
Cyclosporine | Stable maintenance dose in heart transplant recipients | 200 mg (tablets) once daily x 10 days [The tablet refers to a non-commercial tablet formulation without polymer.] | ↑ cyclosporine whole blood trough concentrations Cyclosporine dose reductions of up to 29% were required
Tacrolimus | 0.05-mg/kg single oral dose | 400 mg (oral suspension) twice daily × 7 days | ↑ 121% (2.21; 2.01-2.42) | ↑ 358% (4.58; 4.03-5.19)
Simvastatin | 40-mg single oral dose | 100 mg (oral suspension) once daily x 13 days | Simvastatin ↑ 841% (9.41, 7.13-12.44) Simvastatin Acid ↑ 817% (9.17, 7.36-11.43) | Simvastatin ↑ 931% (10.31, 8.40-12.67) Simvastatin Acid ↑634% (7.34, 5.82-9.25)
 |  | 200 mg (oral suspension) once daily x 13 days | Simvastatin ↑ 1041% (11.41, 7.99-16.29) Simvastatin Acid ↑851% (9.51, 8.15-11.10) | Simvastatin ↑ 960% (10.60, 8.63-13.02) Simvastatin Acid ↑ 748% (8.48, 7.04-10.23)
Midazolam | 0.4-mg single intravenous dose [The mean terminal half-life of midazolam was increased from 3 hours to 7 to 11 hours during coadministration with Noxafil.] | 200 mg (oral suspension) twice daily x 7 days | ↑ 30% (1.3; 1.13-1.48) | ↑ 362% (4.62; 4.02-5.3)
 | 0.4-mg single intravenous dose | 400 mg (oral suspension) twice daily x 7 days | ↑62% (1.62; 1.41-1.86) | ↑524% (6.24; 5.43-7.16)
 | 2-mg single oral dose | 200 mg (oral suspension) once daily x 7 days | ↑ 169% (2.69; 2.46-2.93) | ↑ 470% (5.70; 4.82-6.74)
 | 2-mg single oral dose | 400 mg (oral suspension) twice daily x 7 days | ↑ 138% (2.38; 2.13-2.66) | ↑ 397% (4.97; 4.46-5.54)
Rifabutin | 300 mg once daily x 17 days | 200 mg (tablets) once daily × 10 days | ↑ 31% (1.31; 1.10-1.57) | ↑ 72% (1.72;1.51-1.95)
Phenytoin | 200 mg once daily PO x 10 days | 200 mg (tablets) once daily x 10 days | ↑ 16% (1.16; 0.85-1.57) | ↑ 16% (1.16; 0.84-1.59)
Ritonavir | 100 mg once daily x 14 days | 400 mg (oral suspension) twice daily x 7 days | ↑ 49% (1.49; 1.04-2.15) | ↑ 80% (1.8;1.39-2.31)
Atazanavir | 300 mg once daily x 14 days | 400 mg (oral suspension) twice daily x 7 days | ↑ 155% (2.55; 1.89-3.45) | ↑ 268% (3.68; 2.89-4.70)
Atazanavir/ ritonavir boosted regimen | 300 mg/100 mg once daily x 14 days | 400 mg (oral suspension) twice daily x 7 days | ↑ 53% (1.53; 1.13-2.07) | ↑ 146% (2.46; 1.93-3.13)

Additional clinical studies demonstrated that no clinically significant effects on zidovudine, lamivudine, indinavir, or caffeine were observed when administered with Noxafil 200 mg once daily; therefore, no dose adjustments are required for these coadministered drugs when coadministered with posaconazole 200 mg once daily.

Excretion:

Following administration of Noxafil oral suspension, posaconazole is predominantly eliminated in the feces (71% of the radiolabeled dose up to 120 hours) with the major component eliminated as parent drug (66% of the radiolabeled dose). Renal clearance is a minor elimination pathway, with 13% of the radiolabeled dose excreted in urine up to 120 hours (<0.2% of the radiolabeled dose is parent drug).

Posaconazole delayed-release tablet is eliminated with a mean half-life (t½) ranging between 26 to 31 hours.

Posaconazole oral suspension is eliminated with a mean half-life (t½) of 35 hours (range: 20-66 hours).

Specific Populations

No clinically significant differences in the pharmacokinetics of posaconazole were observed based on age, sex, renal impairment, and indication (prophylaxis or treatment).

Race/Ethnicity:

In a population pharmacokinetic analysis of posaconazole, AUC was found to be 25% higher in Chinese patients relative to patients from other races/ethnicities. This higher exposure is not expected to be clinically relevant given the expected variability in posaconazole exposure.

Patients Weighing More Than 120 kg:

Weight has a clinically significant effect on posaconazole clearance. Relative to 70 kg patients, the Cavg is decreased by 25% in patients greater than 120 kg. Patients administered posaconazole weighing more than 120 kg may be at higher risk for lower posaconazole plasma concentrations compared to lower weight patients [see Use in Specific Populations (8.10)].

12.4 Microbiology

Mechanism of Action:

Posaconazole blocks the synthesis of ergosterol, a key component of the fungal cell membrane, through the inhibition of cytochrome P-450 dependent enzyme lanosterol 14α-demethylase responsible for the conversion of lanosterol to ergosterol in the fungal cell membrane. This results in an accumulation of methylated sterol precursors and a depletion of ergosterol within the cell membrane thus weakening the structure and function of the fungal cell membrane. This may be responsible for the antifungal activity of posaconazole.

Resistance:

Clinical isolates of Candida albicans and Candida glabrata with decreased susceptibility to posaconazole were observed in oral swish samples taken during prophylaxis with posaconazole and fluconazole, suggesting a potential for development of resistance. These isolates also showed reduced susceptibility to other azoles, suggesting cross-resistance between azoles. The clinical significance of this finding is not known.

Antimicrobial Activity:

Posaconazole has been shown to be active against most isolates of the following microorganisms, both in vitro and in clinical infections [see Indications and Usage (1)].

Microorganisms:

Aspergillus spp. and Candida spp.

Susceptibility Testing:

For specific information regarding susceptibility test interpretive criteria and associated test methods and quality control standards recognized by FDA for this drug, please see:
https://www.fda.gov/STIC .

13 NONCLINICAL TOXICOLOGY

13.1 Carcinogenesis, Mutagenesis, Impairment of Fertility

Carcinogenesis

No drug-related neoplasms were recorded in rats or mice treated with posaconazole for 2 years at doses higher than the clinical dose. In a 2-year carcinogenicity study, rats were given posaconazole orally at doses up to 20 mg/kg (females), or 30 mg/kg (males). These doses are equivalent to 3.9- or 3.5-times the exposure achieved with a 400-mg twice daily oral suspension regimen, respectively, based on steady-state AUC in healthy volunteers administered a high-fat meal (400-mg twice daily oral suspension regimen). In the mouse study, mice were treated at oral doses up to 60 mg/kg/day or 4.8-times the exposure achieved with a 400-mg twice daily oral suspension regimen.

Mutagenesis

Posaconazole was not genotoxic or clastogenic when evaluated in bacterial mutagenicity (Ames), a chromosome aberration study in human peripheral blood lymphocytes, a Chinese hamster ovary cell mutagenicity study, and a mouse bone marrow micronucleus study.

Impairment of Fertility

Posaconazole had no effect on fertility of male rats at a dose up to 180 mg/kg (1.7 x the 400-mg twice daily oral suspension regimen based on steady-state plasma concentrations in healthy volunteers) or female rats at a dose up to 45 mg/kg (2.2 x the 400-mg twice daily oral suspension regimen).

13.2 Animal Toxicology and/or Pharmacology

In a nonclinical study using intravenous administration of posaconazole in very young dogs (dosed from 2 to 8 weeks of age), an increase in the incidence of brain ventricle enlargement was observed in treated animals as compared with concurrent control animals. No difference in the incidence of brain ventricle enlargement between control and treated animals was observed following the subsequent 5-month treatment-free period. There were no neurologic, behavioral or developmental abnormalities in the dogs with this finding, and a similar brain finding was not seen with oral posaconazole administration to juvenile dogs (4 days to 9 months of age). There were no drug-related increases in the incidence of brain ventricle enlargement when treated, and control animals were compared in a separate study of 10-week-old dogs dosed with intravenous posaconazole for 13 weeks with a 9-week recovery period or a follow-up study of 31-week-old dogs dosed for 3 months.

14 CLINICAL STUDIES

14.1 Treatment of Invasive Aspergillosis with Noxafil Injection and Noxafil Delayed-Release Tablets

Aspergillosis Treatment Study (NCT01782131) was a randomized, double-blind, controlled trial which evaluated the safety and efficacy of Noxafil injection and Noxafil delayed-release tablets versus voriconazole for primary treatment of invasive fungal disease caused by Aspergillus species. Eligible patients had proven, probable, or possible invasive fungal infections per the European Organization for Research and Treatment of Cancer/Mycoses Study Group, EORTC/MSG criteria. Patients were stratified by risk for mortality or poor outcome where high risk included a history of allogeneic bone marrow transplant, liver transplant, or relapsed leukemia undergoing salvage chemotherapy. The median age of patients was 57 years (range 14-91 years), with 27.8% of patients aged ≥65 years; 5 patients were pediatric patients 14-16 years of age, of whom 3 were treated with Noxafil and 2 with voriconazole. The majority of patients were male (59.8%) and white (67.1%). With regard to risk factors for invasive aspergillosis, approximately two-thirds of the patients in the study had a recent history of neutropenia, while approximately 20% with a history of an allogeneic stem cell transplant. Over 80% of subjects in each treatment group had infection limited to the lower respiratory tract (primarily lung), while approximately 11% to 13% also had infection in another organ. Invasive aspergillosis was proven or probable in 58.1% of patients as classified by independent adjudicators blinded to study treatment assignment. At least one Aspergillus species was identified in 21% of the patients; A. fumigatus and A. flavus were the most common pathogens identified.

Patients randomized to receive Noxafil were given a dose of 300 mg once daily (twice daily on Day 1) IV or tablet. Patients randomized to receive voriconazole were given a dose of 6 mg/kg twice daily Day 1 followed by 4 mg/kg twice daily IV, or oral 300 mg twice daily Day 1 followed by 200 mg twice daily. The recommended initial route of administration was IV; however, patients could begin oral therapy if clinically stable and able to tolerate oral dosing. The transition from IV to oral therapy occurred when the patient was clinically stable. The protocol recommended duration of therapy was 84 days with a maximum allowed duration of 98 days. Median treatment duration was 67 days for Noxafil patients and 64 days for voriconazole patients. Overall, 55% to 60% of patients began treatment with the IV formulation with a median duration of 9 days for the initial IV dosing.

The Intent to Treat (ITT) population included all patients randomized and receiving at least one dose of study treatment. All-cause mortality through Day 42 in the overall population (ITT) was 15.3% for Noxafil patients compared to 20.6% for voriconazole patients for an adjusted treatment difference of -5.3% with a 95% confidence interval of -11.6 to 1.0%. Consistent results were seen in patients with proven or probable invasive aspergillosis per EORTC criteria (see Table 21).

Table 21: Noxafil Injection and Noxafil Delayed-Release Tablets Invasive Aspergillosis Treatment Study: All-Cause Mortality Through Day 42
 | Noxafil Injection and Delayed-Release Tablets |  | Voriconazole
Population | N | n (%) | N | n (%) | Difference [Adjusted treatment difference based on Miettinen and Nurminen’s method stratified by randomization factor (risk for mortality/poor outcome), using Cochran-Mantel-Haenszel weighting scheme.] (95% CI)
Intent to Treat | 288 | 44 (15.3) | 287 | 59 (20.6) | -5.3 (-11.6, 1.0)
Proven/Probable Invasive Aspergillosis | 163 | 31 (19.0) | 171 | 32 (18.7) | 0.3 (-8.2, 8.8)

Global clinical response at Week 6 was assessed by a blinded, independent adjudication committee based upon prespecified clinical, radiologic, and mycologic criteria. In the subgroup of patients with proven or probable invasive aspergillosis per EORTC criteria, the global clinical response of success (complete or partial response) at Week 6 was seen in 44.8% for Noxafil-treated patients compared to 45.6% for voriconazole-treated patients (see Table 22).

Table 22: Noxafil Injection and Noxafil Delayed-Release Tablets Invasive Aspergillosis Treatment Study: Successful Global Clinical Response [Successful Global Clinical Response was defined as survival with a partial or complete response.] at Week 6
 | Posaconazole |  | Voriconazole
Population | N | Success | N | Success | Difference [Adjusted treatment difference based on Miettinen and Nurminen’s method stratified by randomization factor (risk for mortality/poor outcome), using Cochran-Mantel-Haenszel weighting scheme.] (95% CI)
Proven/Probable Invasive Aspergillosis | 163 | 73 (44.8) | 171 | 78 (45.6) | -0.6 (-11.2, 10.1)

14.2 Prophylaxis of Aspergillus and Candida Infections with Noxafil Oral Suspension

Two randomized, controlled studies were conducted using Noxafil as prophylaxis for the prevention of invasive fungal infections (IFIs) among patients at high risk due to severely compromised immune systems.

The first study (Noxafil Oral Suspension Study 1) was a randomized, double-blind trial that compared Noxafil oral suspension (200 mg three times a day) with fluconazole capsules (400 mg once daily) as prophylaxis against invasive fungal infections in allogeneic hematopoietic stem cell transplant (HSCT) recipients with Graft versus Host Disease (GVHD). Efficacy of prophylaxis was evaluated using a composite endpoint of proven/probable IFIs, death, or treatment with systemic antifungal therapy (patients may have met more than one of these criteria). This assessed all patients while on study therapy plus 7 days and at 16 weeks post-randomization. The mean duration of therapy was comparable between the 2 treatment groups (80 days, Noxafil oral suspension; 77 days, fluconazole). Table 23 contains the results from Noxafil Oral Suspension Study 1.

Table 23: Results from Blinded Clinical Study in Prophylaxis of IFI in All Randomized Patients with Hematopoietic Stem Cell Transplant (HSCT) and Graft-vs.-Host Disease (GVHD): Noxafil Oral Suspension Study 1
 | Posaconazole n=301 | Fluconazole n=299
On therapy plus 7 days
Clinical Failure [Patients may have met more than one criterion defining failure.] | 50 (17%) | 55 (18%)
Failure due to:
Proven/Probable IFI | 7 (2%) | 22 (7%)
(Aspergillus) | 3 (1%) | 17 (6%)
(Candida) | 1 (<1%) | 3 (1%)
(Other) | 3 (1%) | 2 (1%)
All Deaths | 22 (7%) | 24 (8%)
Proven/probable fungal infection prior to death | 2 (<1%) | 6 (2%)
SAF [Use of systemic antifungal therapy (SAF) criterion is based on protocol definitions (empiric/IFI usage >4 consecutive days).] | 27 (9%) | 25 (8%)
Through 16 weeks
Clinical Failure, [95% confidence interval (posaconazole-fluconazole) = (-11.5%, +3.7%).] | 99 (33%) | 110 (37%)
Failure due to:
Proven/Probable IFI | 16 (5%) | 27 (9%)
(Aspergillus) | 7 (2%) | 21 (7%)
(Candida) | 4 (1%) | 4 (1%)
(Other) | 5 (2%) | 2 (1%)
All Deaths | 58 (19%) | 59 (20%)
Proven/probable fungal infection prior to death | 10 (3%) | 16 (5%)
SAF | 26 (9%) | 30 (10%)
Event free lost to follow-up [Patients who are lost to follow-up (not observed for 112 days), and who did not meet another clinical failure endpoint. These patients were considered failures.] | 24 (8%) | 30 (10%)

The second study (Noxafil Oral Suspension Study 2) was a randomized, open-label study that compared Noxafil oral suspension (200 mg 3 times a day) with fluconazole suspension (400 mg once daily) or itraconazole oral solution (200 mg twice a day) as prophylaxis against IFIs in neutropenic patients who were receiving cytotoxic chemotherapy for AML or MDS. As in Noxafil Oral Suspension Study 1, efficacy of prophylaxis was evaluated using a composite endpoint of proven/probable IFIs, death, or treatment with systemic antifungal therapy (Patients might have met more than one of these criteria). This study assessed patients while on treatment plus 7 days and 100 days postrandomization. The mean duration of therapy was comparable between the 2 treatment groups (29 days, posaconazole; 25 days, fluconazole or itraconazole). Table 24 contains the results from Noxafil Oral Suspension Study 2.

Table 24: Results from Open-Label Clinical Study 2 in Prophylaxis of IFI in All Randomized Patients with Hematologic Malignancy and Prolonged Neutropenia: Noxafil Oral Suspension Study 2
 | Posaconazole n=304 | Fluconazole/Itraconazole n=298
On therapy plus 7 days
Clinical Failure [95% confidence interval (posaconazole-fluconazole/itraconazole) = (-22.9%, -7.8%).] , [Patients may have met more than one criterion defining failure.] | 82 (27%) | 126 (42%)
Failure due to:
Proven/Probable IFI | 7 (2%) | 25 (8%)
(Aspergillus) | 2 (1%) | 20 (7%)
(Candida) | 3 (1%) | 2 (1%)
(Other) | 2 (1%) | 3 (1%)
All Deaths | 17 (6%) | 25 (8%)
Proven/probable fungal infection prior to death | 1 (<1%) | 2 (1%)
SAF [Use of systemic antifungal therapy (SAF) criterion is based on protocol definitions (empiric/IFI usage >3 consecutive days).] | 67 (22%) | 98 (33%)
Through 100 days postrandomization
Clinical Failure | 158 (52%) | 191 (64%)
Failure due to:
Proven/Probable IFI | 14 (5%) | 33 (11%)
(Aspergillus) | 2 (1%) | 26 (9%)
(Candida) | 10 (3%) | 4 (1%)
(Other) | 2 (1%) | 3 (1%)
All Deaths | 44 (14%) | 64 (21%)
Proven/probable fungal infection prior to death | 2 (1%) | 16 (5%)
SAF | 98 (32%) | 125 (42%)
Event free lost to follow-up [Patients who are lost to follow-up (not observed for 100 days), and who did not meet another clinical failure endpoint. These patients were considered failures.] | 34 (11%) | 24 (8%)

In summary, 2 clinical studies of prophylaxis were conducted with the Noxafil oral suspension. As seen in the accompanying tables (Tables 23 and 24), clinical failure represented a composite endpoint of breakthrough IFI, mortality and use of systemic antifungal therapy. In Noxafil Oral Suspension Study 1 (Table 23), the clinical failure rate of posaconazole (33%) was similar to fluconazole (37%), (95% CI for the difference posaconazole–comparator -11.5% to 3.7%) while in Noxafil Oral Suspension Study 2 (Table 24) clinical failure was lower for patients treated with posaconazole (27%) when compared to patients treated with fluconazole or itraconazole (42%), (95% CI for the difference posaconazole–comparator -22.9% to -7.8%).

All-cause mortality was similar at 16 weeks for both treatment arms in Noxafil Oral Suspension Study 1 [POS 58/301 (19%) vs. FLU 59/299 (20%)]; all-cause mortality was lower at 100 days for Noxafil-treated patients in Noxafil Oral Suspension Study 2 [POS 44/304 (14%) vs. FLU/ITZ 64/298 (21%)]. Both studies demonstrated fewer breakthrough infections caused by Aspergillus species in patients receiving Noxafil prophylaxis when compared to patients receiving fluconazole or itraconazole.

14.3 Treatment of Oropharyngeal Candidiasis with Noxafil Oral Suspension

Noxafil Oral Suspension Study 3 was a randomized, controlled, evaluator-blinded study in HIV-infected patients with oropharyngeal candidiasis. Patients were treated with Noxafil or fluconazole oral suspension (both Noxafil and fluconazole were given as follows: 100 mg twice a day for 1 day followed by 100 mg once a day for 13 days).

Clinical and mycological outcomes were assessed after 14 days of treatment and at 4 weeks after the end of treatment. Patients who received at least 1 dose of study medication and had a positive oral swish culture of Candida species at baseline were included in the analyses (see Table 25). The majority of the subjects had C. albicans as the baseline pathogen.

Clinical success at Day 14 (complete or partial resolution of all ulcers and/or plaques and symptoms) and clinical relapse rates (recurrence of signs or symptoms after initial cure or improvement) 4 weeks after the end of treatment were similar between the treatment arms (see Table 25).

Mycologic eradication rates (absence of colony forming units in quantitative culture at the end of therapy, Day 14), as well as mycologic relapse rates (4 weeks after the end of treatment) were also similar between the treatment arms (see Table 25).

Table 25: Noxafil Oral Suspension Clinical Success, Mycological Eradication, and Relapse Rates in Oropharyngeal Candidiasis
 | Noxafil | Fluconazole
Clinical Success at End of Therapy (Day 14) | 155/169 (91.7%) | 148/160 (92.5%)
Clinical Relapse (4 Weeks after End of Therapy) | 45/155 (29.0%) | 52/148 (35.1%)
Mycological Eradication (absence of CFU) at End of Therapy (Day 14) | 88/169 (52.1%) | 80/160 (50.0%)
Mycological Relapse (4 Weeks after End of Treatment) | 49/88 (55.6%) | 51/80 (63.7%)

Mycologic response rates, using a criterion for success as a posttreatment quantitative culture with ≤20 colony forming units (CFU/mL) were also similar between the two groups (Noxafil 68.0%, fluconazole 68.1%). The clinical significance of this finding is unknown.

14.4 Noxafil Oral Suspension Treatment of Oropharyngeal Candidiasis Refractory to Treatment with Fluconazole or Itraconazole

Noxafil Oral Suspension Study 4 was a noncomparative study of Noxafil oral suspension in HIV-infected subjects with OPC that was refractory to treatment with fluconazole or itraconazole. An episode of OPC was considered refractory if there was failure to improve or worsening of OPC after a standard course of therapy with fluconazole greater than or equal to 100 mg/day for at least 10 consecutive days or itraconazole 200 mg/day for at least 10 consecutive days and treatment with either fluconazole or itraconazole had not been discontinued for more than 14 days prior to treatment with Noxafil. Of the 199 subjects enrolled in this study, 89 subjects met these strict criteria for refractory infection.

Forty-five subjects with refractory OPC were treated with Noxafil oral suspension 400 mg twice daily for 3 days, followed by 400 mg once daily for 25 days with an option for further treatment during a 3-month maintenance period. Following a dosing amendment, a further 44 subjects were treated with Noxafil 400 mg twice daily for 28 days. The efficacy of Noxafil was assessed by the clinical success (cure or improvement) rate after 4 weeks of treatment. The clinical success rate was 74.2% (66/89). The clinical success rates for both the original and the amended dosing regimens were similar (73.3% and 75.0%, respectively).

16 HOW SUPPLIED/STORAGE AND HANDLING

16.1 How Supplied

Posaconazole Delayed-Release Tablets

Posaconazole delayed-release tablets are available as yellow, coated, oblong, debossed with "100" on one side containing 100 mg of posaconazole. Bottles with child-resistant closures of 60 delayed-release tablets (NDC 0254-2045-02).

Posaconazole Oral Suspension

Posaconazole oral suspension is available as a white, cherry-flavored suspension in 4-ounce (123 mL) amber glass bottles with child-resistant closures (NDC 0254-1016-36) containing 105 mL of suspension (40 mg of posaconazole per mL).

Supplied with each oral suspension bottle is a plastic dosing spoon calibrated for measuring 2.5-mL and 5-mL doses.

16.2 Storage and Handling

Posaconazole Delayed-Release Tablets

Store at 20°C to 25°C (68°F to 77°F), excursions permitted to 15°C to 30°C (59°F to 86°F) [see USP Controlled Room Temperature].

Posaconazole Oral Suspension

Store at 25°C (77°F); excursions permitted to 15 to 30°C (59 to 86°F) [see USP Controlled Room Temperature]. DO NOT FREEZE.

17 PATIENT COUNSELING INFORMATION

Advise the patient to read the FDA-approved patient labeling (Patient Information).

Important Administration Instructions

Posaconazole Delayed-Release Tablets

Advise patients that Posaconazole delayed-release tablets must be swallowed whole and not divided, crushed, or chewed.

Instruct patients that if they miss a dose, they should take it as soon as they remember. If they do not remember until it is within 12 hours of the next dose, they should be instructed to skip the missed dose and go back to the regular schedule. Patients should not double their next dose or take more than the prescribed dose.

Posaconazole Oral Suspension

Advise patients to take each dose of Posaconazole oral suspension during or immediately (i.e., within 20 minutes) following a full meal. In patients who cannot eat a full meal, each dose of Posaconazole oral suspension should be administered with a liquid nutritional supplement or an acidic carbonated beverage (e.g., ginger ale) in order to enhance absorption.

Instruct patients that if they miss a dose, they should take it as soon as they remember. However, if it is almost time for the next dose, they should be instructed to skip the missed dose and go back to the regular schedule. Patients should not double their next dose or take more than the prescribed dose.

Drug Interactions

Advise patients to inform their physician immediately if they:

- develop severe diarrhea or vomiting.
- are currently taking drugs that are known to prolong the QTc interval and are metabolized through CYP3A4.
- are currently taking a cyclosporine or tacrolimus, or they notice swelling in an arm or leg or shortness of breath.
- are taking other drugs or before they begin taking other drugs as certain drugs can decrease or increase the plasma concentrations of posaconazole.

Serious and Potentially Serious Adverse Reactions

Advise patients to inform their physician immediately if they:

- notice a change in heart rate or heart rhythm or have a heart condition or circulatory disease. Posaconazole can be administered with caution to patients with potentially proarrhythmic conditions.
- are pregnant, plan to become pregnant, or are nursing.
- have liver disease or develop itching, nausea or vomiting, their eyes or skin turn yellow, they feel more tired than usual or feel like they have the flu.
- have ever had an allergic reaction to other antifungal medicines such as ketoconazole, fluconazole, itraconazole, or voriconazole.

Manufactured for: Endo USA, Malvern, PA 19355

Delayed-Release Tablets: Manuf. by: N. V. Organon, Kloosterstraat 6, 5349 AB Oss, Netherlands

Oral Suspension: Manuf. by: Patheon Inc., Whitby, Ontario, Canada L1N5Z5

The trademarks referenced herein are owned by their respective companies.

uspi-gmk5592-mf-2411r008

OS1016-01-78-05

Patient Information
Posaconazole delayed-release tablets
Posaconazole oral suspension

What is posaconazole?
Posaconazole (which refers to delayed-release tablets and oral suspension) is a prescription medicine used in adults and children to help prevent or treat fungal infections that can spread throughout your body (invasive fungal infections). These infections are caused by fungi called Aspergillus or Candida. Posaconazole is used in people who have an increased chance of getting these infections due to a weak immune system. These include people who have had a hematopoietic stem cell transplantation (bone marrow transplant) with graft versus host disease or those with a low white blood cell count due to chemotherapy for blood cancers (hematologic malignancies).
Posaconazole delayed-release tablets are used for:

- prevention of fungal infections in adults and children 2 years of age and older who weigh greater than 88 lbs (40 kg).
- treatment of fungal infections in adults and children 13 years of age and older.

Posaconazole oral suspension is used for:

- prevention of fungal infections in adults and children 13 years of age and older.

Posaconazole oral suspension is also used to treat a fungal infection called “thrush” caused by Candida in your mouth or throat area. Posaconazole oral suspension can be used as the first treatment for thrush, or as another treatment for thrush after itraconazole or fluconazole treatment has not worked.
Posaconazole oral suspension is for adults and children 13 years of age and older.
It is not known if posaconazole is safe and effective in children under 2 years of age.

Who should not take posaconazole?
Do not take posaconazole if you:

- are allergic to posaconazole, any of the ingredients in posaconazole, or other azole antifungal medicines. See the end of this leaflet for a complete list of ingredients in posaconazole.
- are taking any of the following medicines:
  - sirolimus
  - pimozide
  - quinidine
  - certain statin medicines that lower cholesterol (atorvastatin, lovastatin, simvastatin)
  - ergot alkaloids (ergotamine, dihydroergotamine)
- have chronic lymphocytic leukemia (CLL) or small lymphocytic lymphoma (SLL) and you have just started taking venetoclax or your venetoclax dose is being slowly increased.

Ask your healthcare provider or pharmacist if you are not sure if you are taking any of these medicines.
Do not start taking a new medicine without talking to your healthcare provider or pharmacist.

What should I tell my healthcare provider before taking posaconazole?
Before you take posaconazole, tell your healthcare provider if you:

- are taking certain medicines that lower your immune system like cyclosporine or tacrolimus.
- are taking certain drugs for HIV infection, such as ritonavir, atazanavir, efavirenz, or fosamprenavir. Efavirenz and fosamprenavir can cause a decrease in the posaconazole levels in your body. Efavirenz and fosamprenavir should not be taken with posaconazole.
- are taking midazolam, a hypnotic and sedative medicine.
- are taking vincristine, vinblastine and other "vinca alkaloids" (medicines used to treat cancer).
- are taking venetoclax, a medicine used to treat cancer.
- have or had liver problems.
- have or had kidney problems.
- have or had an abnormal heart rate or rhythm, heart problems, or blood circulation problems.
- are pregnant or plan to become pregnant. It is not known if posaconazole will harm your unborn baby.
- are breastfeeding or plan to breastfeed. It is not known if posaconazole passes into your breast milk. You and your healthcare provider should decide if you will take posaconazole or breastfeed. You should not do both.

Tell your healthcare provider about all the medicines you take, including prescription and over-the-counter medicines, vitamins, and herbal supplements. Posaconazole can affect the way other medicines work, and other medicines can affect the way posaconazole works, and can cause serious side effects.
Especially tell your healthcare provider if you take:

- rifabutin or phenytoin. If you are taking these medicines, you should not take Posaconazole delayed-release tablets or Posaconazole oral suspension.
- cimetidine or esomeprazole. If you are taking these medicines, you should not take Posaconazole oral suspension.

Ask your healthcare provider or pharmacist for a list of these medicines if you are not sure.
Know the medicines you take. Keep a list of them with you to show your healthcare provider or pharmacist when you get a new medicine.

How will I take posaconazole?

- Do not switch between Posaconazole oral suspension and Posaconazole delayed-release tablets or Noxafil PowderMix for delayed-release oral suspension.
- Take posaconazole exactly as your healthcare provider tells you to take it.
- Your healthcare provider will tell you how much posaconazole to take and when to take it.
- Take posaconazole for as long as your healthcare provider tells you to take it.
- If you take too much posaconazole, call your healthcare provider or go to the nearest hospital emergency room right away.
- Posaconazole delayed-release tablets:
  - Take Posaconazole delayed-release tablets with or without food.
  - Take Posaconazole delayed-release tablets whole. Do not break, crush, or chew Posaconazole delayed-release tablets before swallowing. If you cannot swallow Posaconazole delayed-release tablets whole, tell your healthcare provider. You may need a different medicine.
  - If you miss a dose, take it as soon as you remember and then take your next scheduled dose at its regular time. If it is within 12 hours of your next dose, do not take the missed dose. Skip the missed dose and go back to your regular schedule. Do not double your next dose or take more than your prescribed dose.
- Posaconazole oral suspension:
  - Shake Posaconazole oral suspension well before use.
  - Take each dose of Posaconazole oral suspension during or within 20 minutes after a full meal. If you cannot eat a full meal, take each dose of Posaconazole oral suspension with a liquid nutritional supplement or an acidic carbonated beverage, like ginger ale.
  - A measured dosing spoon comes with your Posaconazole oral suspension and is marked for doses of 2.5 mL and 5 mL. See Figure A.
  - Rinse the spoon with water after each dose of Posaconazole oral suspension and before you store it away.
  - If you miss a dose, take it as soon as you remember. However, if it is almost time for the next dose, skip the missed dose and go back to the regular dosing schedule. Do not take a double dose to make up for the missed dose.

Follow the instructions from your healthcare provider on how much posaconazole you should take and when to take it.

What are the possible side effects of posaconazole?
Posaconazole may cause serious side effects, including:

- drug interactions with cyclosporine or tacrolimus. If you take posaconazole with cyclosporine or tacrolimus, your blood levels of cyclosporine or tacrolimus may increase. Serious side effects can happen in your kidney or brain if you have high levels of cyclosporine or tacrolimus in your blood. Your healthcare provider should do blood tests to check your levels of cyclosporine or tacrolimus if you are taking these medicines while taking posaconazole. Tell your healthcare provider right away if you have swelling in your arm or leg or shortness of breath.
- problems with the electrical system of your heart (arrhythmias and QTc prolongation). Certain medicines used to treat fungus called azoles, including posaconazole, the active ingredient in posaconazole, may cause heart rhythm problems. People who have certain heart problems or who take certain medicines have a higher chance for this problem. Tell your healthcare provider right away if your heartbeat becomes fast or irregular.
- changes in body salt (electrolytes) levels in your blood. Your healthcare provider should check your electrolytes while you are taking posaconazole.
- new or worsening high blood pressure and low potassium levels in your blood (pseudoaldosteronism). Your healthcare provider should check your blood pressure and potassium levels.
- liver problems. Some people who also have other serious medical problems may have severe liver problems that may lead to death, especially if you take certain doses of posaconazole. Your healthcare provider should do blood tests to check your liver while you are taking posaconazole. Call your healthcare provider right away if you have any of the following symptoms of liver problems:

- itchy skin
- nausea or vomiting
- yellowing of your eyes or skin

- feeling very tired
- flu-like symptoms

- increased amounts of midazolam in your blood. If you take posaconazole with midazolam, posaconazole increases the amount of midazolam in your blood. This can make your sleepiness last longer. Your healthcare provider should check you closely for side effects if you take midazolam with posaconazole.

The most common side effects of posaconazole include:

- diarrhea
- nausea
- fever
- vomiting

- headache
- coughing
- low potassium levels in the blood

If you take Posaconazole delayed-release tablets or Posaconazole oral suspension, tell your healthcare provider right away if you have diarrhea or vomiting.
Tell your healthcare provider if you have any side effect that bothers you or that does not go away.
These are not all the possible side effects of posaconazole. For more information, ask your healthcare provider or pharmacist.
Call your doctor for medical advice about side effects. You may report side effects to FDA at 1-800-FDA-1088.

How should I store posaconazole?
Posaconazole delayed-release tablets

- Store Posaconazole delayed-release tablets at room temperature between 68°F to 77°F (20°C to 25°C).

Posaconazole oral suspension

- Store Posaconazole oral suspension at room temperature between 68°F to 77°F (20°C to 25°C).
- Do not freeze Posaconazole oral suspension.

Safely throw away medicine that is out of date or no longer needed.
Keep posaconazole and all medicines out of the reach of children.

General information about the safe and effective use of posaconazole.
Medicines are sometimes prescribed for purposes other than those listed in a Patient Information leaflet. Do not use posaconazole for a condition for which it was not prescribed. Do not give posaconazole to other people, even if they have the same symptoms that you have. It may harm them. You can ask your pharmacist or healthcare provider for information about posaconazole that is written for health professionals.

What are the ingredients in posaconazole?
Active ingredient: posaconazole
Inactive ingredients:
Posaconazole delayed-release tablets: croscarmellose sodium, hydroxypropylcellulose, hypromellose acetate succinate, iron oxide yellow, Macrogol/PEG 3350, magnesium stearate, microcrystalline cellulose, polyvinyl alcohol partially hydrolyzed, silicon dioxide, talc, and titanium dioxide.
Posaconazole oral suspension: artificial cherry flavor, citric acid monohydrate, glycerin, liquid glucose, polysorbate 80, purified water, simethicone, sodium benzoate, sodium citrate dihydrate, titanium dioxide, and xanthan gum.
Manufactured for: Endo USA, Malvern, PA 19355
Delayed-Release Tablets: Manuf. by: N. V. Organon, Kloosterstraat 6, 5349 AB Oss, Netherlands
Oral Suspension: Manuf. by: Patheon Inc., Whitby, Ontario, Canada L1N5Z5
usppi-gmk5592-mf-2411r006
PI1016-01-78-04

This Patient Information has been approved by the U.S. Food and Drug Administration.

Revised: 11/2024

PRINCIPAL DISPLAY PANEL - 100 mg Tablet Bottle Label

NDC 0254-2045-02

Posaconazole
Delayed-Release
Tablets

100 mg

Each tablet contains 100 mg posaconazole.

Attention: Posaconazole Oral Suspension and
Delayed-Release Tablets are NOT substitutable
due to differences in the dosing of each formulation.

Rx only

60 Tablets

endo®

PRINCIPAL DISPLAY PANEL - 105 ML BOTTLE CARTON

NDC 0254-1016-36

105 mL

Posaconazole
Oral Suspension

200 mg/5 mL

Each mL contains: 40 mg posaconazole.

Attention: Posaconazole Oral Suspension
and Delayed-Release Tablets are NOT
substitutable due to differences in the
dosing of each formulation.

SHAKE WELL BEFORE EACH USE.

Take with a meal, or a nutritional supplement,
or an acidic carbonated beverage.

Carton contains measured dosing spoon.

Rx only

endo®